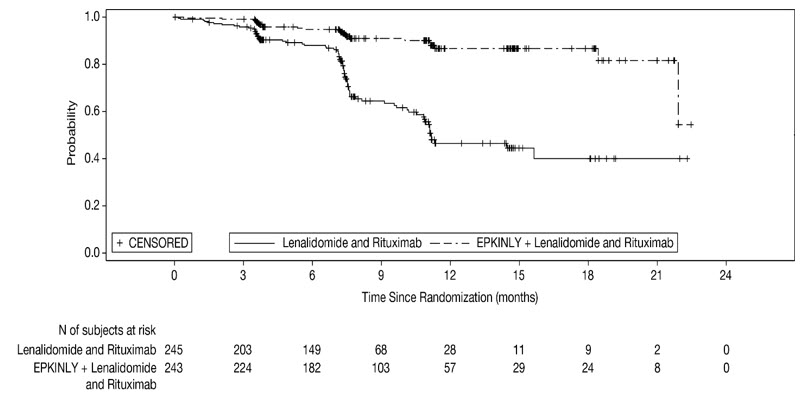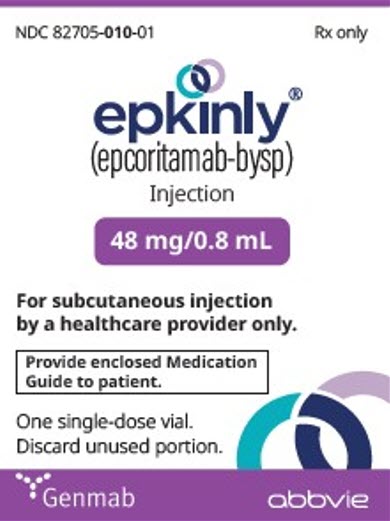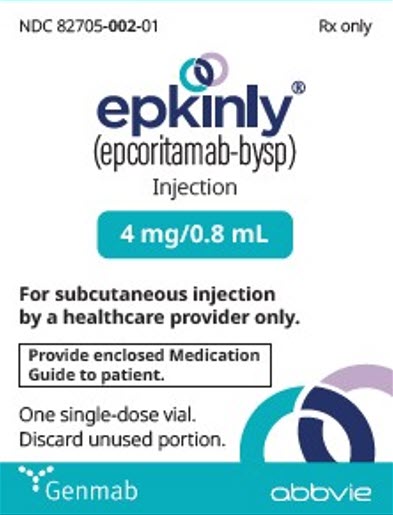 DRUG LABEL: EPKINLY
NDC: 82705-010 | Form: INJECTION, SOLUTION
Manufacturer: Genmab US, Inc.
Category: prescription | Type: HUMAN PRESCRIPTION DRUG LABEL
Date: 20251125

ACTIVE INGREDIENTS: epcoritamab 48 mg/0.8 mL
INACTIVE INGREDIENTS: acetic acid; Sorbitol; polysorbate 80; sodium acetate

HIGHLIGHTS OF PRESCRIBING INFORMATION

These highlights do not include all the information needed to use EPKINLY safely and effectively. See full prescribing information for EPKINLY.
EPKINLY® (epcoritamab-bysp) injection, for subcutaneous use
Initial U.S. Approval: 2023

WARNING: CYTOKINE RELEASE SYNDROME AND IMMUNE EFFECTOR CELL-ASSOCIATED NEUROTOXICITY SYNDROME

See full prescribing information for complete boxed warning.

Cytokine release syndrome (CRS), including serious or fatal reactions, can occur in patients receiving EPKINLY. Initiate treatment with the EPKINLY step-up dosage schedule to reduce the incidence and severity of CRS. Withhold EPKINLY until CRS resolves or permanently discontinue based on severity. (2.1, 2.2, 2.6, 5.1)

Immune Effector Cell-Associated Neurotoxicity Syndrome (ICANS), including life-threatening and fatal reactions, can occur with EPKINLY. Monitor patients for neurological signs or symptoms of ICANS during treatment. Withhold EPKINLY until ICANS resolves or permanently discontinue based on severity. (2.1, 2.2, 2.6, 5.2)

RECENT MAJOR CHANGES

Indications and Usage (1.2) | 11/2025
Dosage and Administration (2.1, 2.2, 2.5, 2.6) | 11/2025
Warnings and Precautions (5.1, 5.2, 5.3, 5.4) | 11/2025
Warnings and Precautions, Infections (5.3) | 9/2025

1 INDICATIONS AND USAGE

EPKINLY is a bispecific CD20-directed CD3 T-cell engager indicated:

- For the treatment of adult patients with relapsed or refractory diffuse large B-cell lymphoma (DLBCL), not otherwise specified, including DLBCL arising from indolent lymphoma, and high-grade B-cell lymphoma after two or more lines of systemic therapy. (1.1)
  This indication is approved under accelerated approval based on response rate and durability of response. Continued approval for this indication may be contingent upon verification and description of clinical benefit in a confirmatory trial(s).
- In combination with lenalidomide and rituximab for the treatment of adult patients with relapsed or refractory follicular lymphoma (FL). (1.2)
- As monotherapy for the treatment of adult patients with relapsed or refractory FL after two or more lines of systemic therapy. (1.2)

2 DOSAGE AND ADMINISTRATION

- For subcutaneous injection only. (2.2)
- Recommended Dosage: (2.2)

DLBCL and High-grade B-cell Lymphoma

Cycle [Cycle = 28 days] | Day | Dose of EPKINLY
Cycle 1 | 1 | Step-up dose 1 | 0.16 mg
Cycle 1 | 8 | Step-up dose 2 | 0.8 mg
Cycle 1 | 15 | First full dose | 48 mg
Cycle 1 | 22 | 48 mg
Cycles 2 and 3 | 1, 8, 15 and 22 | 48 mg
Cycles 4 to 9 | 1 and 15 | 48 mg
Cycle 10 and beyond | 1 | 48 mg

EPKINLY as Monotherapy for FL

Cycle [Cycle = 28 days] | Day | Dose of EPKINLY
Cycle 1 | 1 | Step-up dose 1 | 0.16 mg
Cycle 1 | 8 | Step-up dose 2 | 0.8 mg
Cycle 1 | 15 | Step-up dose 3 | 3 mg
Cycle 1 | 22 | First full dose | 48 mg
Cycles 2 and 3 | 1, 8, 15 and 22 | 48 mg
Cycles 4 to 9 | 1 and 15 | 48 mg
Cycle 10 and beyond | 1 | 48 mg

EPKINLY in Combination with Lenalidomide and Rituximab for FL

Cycle [Cycle = 28 days] | Day | Dose of EPKINLY
Cycle 1 | 1 | Step-up dose 1 | 0.16 mg
Cycle 1 | 8 | Step-up dose 2 | 0.8 mg
Cycle 1 | 15 | Step-up dose 3 | 3 mg
Cycle 1 | 22 | First full dose | 48 mg
Cycles 2 and 3 | 1, 8, 15, and 22 | 48 mg
Cycles 4 to 12 | 1 | 48 mg

- Monitor all patients for signs and symptoms of CRS and ICANS. (2.1)
- Patients with DLBCL or high-grade B-cell lymphoma should be hospitalized for 24 hours after administration of the Cycle 1 Day 15 dosage of 48 mg. (2.1)For patients with FL, assess whether hospitalization or outpatient monitoring is appropriate after administration of the Cycle 1 Day 22 dosage of 48 mg. (2.1)
- Administer premedications, post-medications, and prophylaxis as recommended. (2.4, 2.5)
- Dosages of EPKINLY 0.16 mg and 0.8 mg require dilution prior to administration. (2.7, 2.8)
- See Full Prescribing Information for instructions on preparation and administration. (2.7, 2.8, 2.9, 2.10)

3 DOSAGE FORMS AND STRENGTHS

- Injection: 4 mg/0.8 mL in a single-dose vial. (3)
- Injection: 48 mg/0.8 mL in a single-dose vial. (3)

4 CONTRAINDICATIONS

None. (4)

5 WARNINGS AND PRECAUTIONS

- Infections: Can cause fatal or serious infections. Monitor patients for signs or symptoms of infection, including opportunistic infections, and treat appropriately. (5.3)
- Cytopenias: Monitor complete blood cell counts during treatment. (5.4)
- Embryo-Fetal Toxicity: May cause fetal harm. Advise females of reproductive potential of the potential risk to the fetus and to use effective contraception. (5.5, 8.1, 8.3)

6 ADVERSE REACTIONS

EPKINLY as monotherapy for LBCL or FL: The most common (≥ 20%) adverse reactions are CRS, injection site reactions, fatigue, musculoskeletal pain, fever, diarrhea, COVID-19, rash and abdominal pain. The most common Grade 3 to 4 laboratory abnormalities (≥ 10%) are decreases in lymphocyte count, neutrophil count, hemoglobin, and platelets. (6.1)

EPKINLY in combination with lenalidomide and rituximab for FL: The most common (≥ 20%) adverse reactions are rash, upper respiratory tract infections, fatigue, injection site reactions, constipation, diarrhea, CRS, pneumonia, COVID-19, and fever. The most common Grade 3 to 4 laboratory abnormalities (≥ 10%) are decreased neutrophil count, lymphocyte count, and platelets. (6.1)

To report SUSPECTED ADVERSE REACTIONS, contact Genmab US, Inc. at 1-855-4GENMAB (1-855-443-6622) or FDA at 1-800-FDA-1088 or www.fda.gov/medwatch.

8 USE IN SPECIFIC POPULATIONS

Lactation: Advise not to breastfeed. (8.2)

FULL PRESCRIBING INFORMATION

WARNING: CYTOKINE RELEASE SYNDROME AND IMMUNE EFFECTOR CELL-ASSOCIATED NEUROTOXICITY SYNDROME

Cytokine release syndrome (CRS), including serious or fatal reactions, can occur in patients receiving EPKINLY. Initiate treatment with the EPKINLY step-up dosage schedule to reduce the incidence and severity of CRS. Withhold EPKINLY until CRS resolves or permanently discontinue based on severity [see Dosage and Administration (2.1, 2.2, 2.6) and Warnings and Precautions (5.1)].

Immune Effector Cell-Associated Neurotoxicity Syndrome (ICANS), including life-threatening and fatal reactions, can occur with EPKINLY. Monitor patients for neurological signs or symptoms of ICANS during treatment. Withhold EPKINLY until ICANS resolves or permanently discontinue based on severity [see Dosage and Administration (2.1, 2.2, 2.6) and Warnings and Precautions (5.2)].

1 INDICATIONS AND USAGE

1.1 DLBCL and High-grade B-cell Lymphoma

EPKINLY is indicated for the treatment of adult patients with relapsed or refractory diffuse large B-cell lymphoma (DLBCL), not otherwise specified, including DLBCL arising from indolent lymphoma, and high-grade B-cell lymphoma after two or more lines of systemic therapy.

This indication is approved under accelerated approval based on response rate and durability of response [see Clinical Studies (14.1)]. Continued approval for this indication may be contingent upon verification and description of clinical benefit in a confirmatory trial(s).

1.2 Follicular Lymphoma

EPKINLY is indicated in combination with lenalidomide and rituximab for the treatment of adult patients with relapsed or refractory follicular lymphoma (FL).

EPKINLY is indicated as monotherapy for the treatment of adult patients with relapsed or refractory FL after two or more lines of systemic therapy.

2 DOSAGE AND ADMINISTRATION

2.1 Important Dosing Information

- Certain doses of EPKINLY require dilution prior to administration. There are 2 available methods to prepare diluted EPKINLY:
  - Empty sterile vial method as described in subsection 2.7 [see Dosage and Administration (2.7)], or
  - Sterile syringe method as described in subsection 2.8 [see Dosage and Administration (2.8)].
- Preparation of 3 mg and 48 mg EPKINLY doses does not require dilution. [see Dosage and Administration (2.9)].
- EPKINLY should only be administered by a qualified healthcare professional with appropriate medical support to manage severe reactions such as CRS and ICANS [see Warnings and Precautions (5.1, 5.2)].
- Administer EPKINLY to well-hydrated patients.
- Premedicate before each dose in Cycle 1 [see Dosage and Administration (2.4)].
- Administer EPKINLY subcutaneously according to the recommended step-up dosage schedule to reduce the incidence and severity of CRS [see Dosage and Administration (2.2)].
- Due to the risk of CRS and ICANS, monitor all patients for signs and symptoms [see Dosage and Administration (2.6)].
  - For patients with DLBCL or high-grade B-cell lymphoma:
    Patients should be hospitalized for 24 hours after administration of the Cycle 1 Day 15 dosage of 48 mg [see Dosage and Administration (2.2)].
  - For patients with FL:
    Assess whether hospitalization or outpatient monitoring is appropriate based on comorbidities or other situational factors for the Cycle 1 Day 22 dosage of 48 mg [see Dosage and Administration (2.2)].

2.2 Recommended Dosage

EPKINLY is for subcutaneous injection only.

The recommended DLBCL dosage for Cycle 1 consists of 2 step-up doses, and the recommended FL dosage (monotherapy or in combination with lenalidomide and rituximab) consists of 3 step-up doses.

EPKINLY as Monotherapy:

Administer EPKINLY in 28-day cycles until disease progression or unacceptable toxicity.

Table 1: EPKINLY Dosage Schedule for Patients with DLBCL or High-grade B-cell Lymphoma
Indication | Cycle [Cycle = 28 days.] | Day | Dose of EPKINLY
DLBCL or High-grade B-cell Lymphoma | Cycle 1 | 1 | Step-up dose 1 | 0.16 mg
DLBCL or High-grade B-cell Lymphoma | Cycle 1 | 8 | Step-up dose 2 | 0.8 mg
DLBCL or High-grade B-cell Lymphoma | Cycle 1 | 15 | First full dose | 48 mg
DLBCL or High-grade B-cell Lymphoma | Cycle 1 | 22 | 48 mg
DLBCL or High-grade B-cell Lymphoma | Cycles 2 and 3 | 1, 8, 15 and 22 | 48 mg
DLBCL or High-grade B-cell Lymphoma | Cycles 4 to 9 | 1 and 15 | 48 mg
DLBCL or High-grade B-cell Lymphoma | Cycle 10 and beyond | 1 | 48 mg

Table 2: EPKINLY Dosage Schedule for Patients with FL when Given as Monotherapy
Indication | Cycle [Cycle = 28 days.] | Day | Dose of EPKINLY
Follicular Lymphoma | Cycle 1 | 1 | Step-up dose 1 | 0.16 mg
Follicular Lymphoma | Cycle 1 | 8 | Step-up dose 2 | 0.8 mg
Follicular Lymphoma | Cycle 1 | 15 | Step-up dose 3 | 3 mg
Follicular Lymphoma | Cycle 1 | 22 | First full dose | 48 mg
Follicular Lymphoma | Cycles 2 and 3 | 1, 8, 15 and 22 | 48 mg
Follicular Lymphoma | Cycles 4 to 9 | 1 and 15 | 48 mg
Follicular Lymphoma | Cycle 10 and beyond | 1 | 48 mg

EPKINLY in Combination with Lenalidomide and Rituximab:

Administer EPKINLY in 28-day cycles for a total of 12 cycles or until disease progression or unacceptable toxicity, whichever occurs first.

Table 3: EPKINLY Dosage Schedule in Combination with Lenalidomide and Rituximab for Patients with FL
Indication | Cycle [Cycle = 28 days.] | Day | Dose of EPKINLY
Follicular Lymphoma | Cycle 1 | 1 | Step-up dose 1 | 0.16 mg
Follicular Lymphoma | Cycle 1 | 8 | Step-up dose 2 | 0.8 mg
Follicular Lymphoma | Cycle 1 | 15 | Step-up dose 3 | 3 mg
Follicular Lymphoma | Cycle 1 | 22 | First full dose | 48 mg
Follicular Lymphoma | Cycles 2 and 3 | 1, 8, 15, and 22 | 48 mg
Follicular Lymphoma | Cycles 4 to 12 | 1 | 48 mg

Administer EPKINLY in combination with lenalidomide 20 mg (Days 1 to 21 in Cycles 1 to 12) and rituximab 375 mg/m^2 (Cycles 1 to 5) [see Clinical Studies (14.2)]. Refer to the lenalidomide prescribing information and rituximab prescribing information for the respective dosage recommendations, including lenalidomide dosage recommendations for patients with renal insufficiency.

2.3 Restarting EPKINLY after Dosage Delay

If a dose of EPKINLY is delayed, restart therapy based on the recommendations made in Table 4 for patients with DLBCL or high-grade B-cell lymphoma, or Table 5 for patients with FL [see Dosage and Administration (2.2)].

Table 4: Recommendations for Restarting EPKINLY After Dosage Delay for Patients with DLBCL or High-grade B-cell Lymphoma
Last Dose Administered | Time Since the Last Dose Administered | Action for Next Dose(s) [Administer pretreatment medication prior to EPKINLY dose and monitor patients accordingly [see Dosage and Administration (2.4, 2.6)].]
0.16 mg (e.g., on Cycle 1 Day 1) | More than 8 days | Repeat Cycle 1 schedule starting at step-up dose 1 (0.16 mg). Following the repeat of Cycle 1 schedule, resume the planned treatment schedule.
0.8 mg (e.g., on Cycle 1 Day 8) | 14 days or less | Administer 48 mg, then resume the planned treatment schedule.
0.8 mg (e.g., on Cycle 1 Day 8) | More than 14 days | Repeat Cycle 1 schedule starting at step-up dose 1 (0.16 mg). Following the repeat of Cycle 1 schedule, resume the planned treatment schedule.
48 mg (e.g., on Cycle 1 Day 15 onwards) | 6 weeks or less | Administer 48 mg, then resume the planned treatment schedule.
48 mg (e.g., on Cycle 1 Day 15 onwards) | More than 6 weeks | Repeat Cycle 1 schedule starting at step-up dose 1 (0.16 mg). Following the repeat of Cycle 1 schedule, resume the planned treatment schedule.

Table 5: Recommendations for Restarting EPKINLY After Dosage Delay for Patients with FL
Last Dose Administered | Time Since the Last Dose Administered | Action for Next Dose(s) [Administer pretreatment medication prior to EPKINLY dose and monitor patients accordingly [see Dosage and Administration (2.4, 2.6)].]
0.16 mg (e.g., on Cycle 1 Day 1) | More than 8 days | Repeat Cycle 1 schedule starting at step-up dose 1 (0.16 mg). Following the repeat of Cycle 1 schedule, resume the planned treatment schedule.
0.8 mg (e.g., on Cycle 1 Day 8) | More than 8 days | Repeat Cycle 1 schedule starting at step-up dose 1 (0.16 mg). Following the repeat of Cycle 1 schedule, resume the planned treatment schedule.
3 mg (e.g., on Cycle 1 Day 15) | 14 days or less | Administer 48 mg, then resume the planned treatment schedule.
3 mg (e.g., on Cycle 1 Day 15) | More than 14 days | Repeat Cycle 1 schedule starting at step-up dose 1 (0.16 mg). Following the repeat of Cycle 1 schedule, resume the planned treatment schedule.
48 mg (e.g., on Cycle 1 Day 22 onwards) | 6 weeks or less | Administer 48 mg, then resume the planned treatment schedule.
48 mg (e.g., on Cycle 1 Day 22 onwards) | More than 6 weeks | Repeat Cycle 1 schedule starting at step-up dose 1 (0.16 mg). Following the repeat of Cycle 1 schedule, resume the planned treatment schedule.

2.4 Recommended Pre- and Post-Administration Medications

Administer pre- and post-administration medications as outlined in Table 6 to reduce the risk of CRS [see Warnings and Precautions (5.1)].

Table 6: EPKINLY Pre- and Post-Administration Medications
Cycle | Patients requiring medication | Medication | Administration
Cycle 1 | All patients | - Dexamethasone [Dexamethasone is the preferred corticosteroid when available.] (15 mg oral or intravenous) or Prednisolone (100 mg oral or intravenous) or equivalent | - 30-120 minutes prior to each weekly administration of EPKINLY - And for three consecutive days following each weekly administration of EPKINLY in Cycle 1
Cycle 1 | All patients | - Diphenhydramine (50 mg oral or intravenous) or equivalent - Acetaminophen (650 mg to 1,000 mg oral) | - 30-120 minutes prior to each weekly administration of EPKINLY
Cycle 2+ | Patients who experienced Grade 2 or 3 [Patients will be permanently discontinued from EPKINLY after Grade 4 CRS.] CRS with previous dose | - Dexamethasone (15 mg oral or intravenous) or Prednisolone (100 mg oral or intravenous) or equivalent | - 30-120 minutes prior to next administration of EPKINLY after a Grade 2 or 3 CRS event - And for three consecutive days following the next administration of EPKINLY until EPKINLY is given without subsequent CRS of Grade 2 or higher

2.5 Recommended Prophylaxis

Pneumocystis jirovecii pneumonia (PJP)

Provide PJP prophylaxis during treatment with EPKINLY.

Herpesvirus

Consider providing prophylaxis against herpesvirus during treatment with EPKINLY to prevent herpes simplex and herpes zoster.

Thromboprophylaxis

Refer to the lenalidomide prescribing information for recommendations on prophylaxis for venous and arterial thrombotic events.

2.6 Dosage Modifications and Management of Adverse Reactions

See Tables 7 and 8 for recommended actions for adverse reactions of CRS and ICANS, respectively. See Tables 9 and 10 for recommended actions for other adverse reactions following administration of EPKINLY given as monotherapy and in combination with lenalidomide and rituximab, respectively.

Cytokine Release Syndrome (CRS)

Identify CRS based on clinical presentation [see Warnings and Precautions (5.1)]. Evaluate for and treat other causes of fever, hypotension, and hypoxia.

If CRS is suspected, withhold EPKINLY until CRS resolves. Manage according to the recommendations in Table 7 and consider further management per current practice guidelines. Administer supportive therapy for CRS, which may include intensive care for severe or life-threatening CRS.

Table 7: Recommendations for Management of Cytokine Release Syndrome
Grade [Based on American Society for Transplantation and Cellular Therapy (ASTCT) 2019 grading for CRS.] | Presenting Symptoms | Actions
Grade 1 | Temperature ≥ 100.4°F (38°C) [Premedication may mask fever, therefore if clinical presentation is consistent with CRS, follow these management guidelines.] | - Withhold EPKINLY and manage per current practice guidelines. - Ensure CRS symptoms are resolved prior to next dose of EPKINLY. [Refer to Table 4 or Table 5 for information on restarting EPKINLY after dosage delays [see Dosage and Administration (2.3)].]
Grade 2 | Temperature ≥ 100.4°F (38°C) with: Hypotension not requiring vasopressors and/or Hypoxia requiring low-flow oxygen [Low-flow oxygen defined as oxygen delivered at < 6L/minute; high-flow oxygen defined as oxygen delivered at ≥ 6 L/minute.] by nasal cannula or blow-by. | - Withhold EPKINLY and manage per current practice guidelines. - Ensure CRS symptoms are resolved prior to next dose of EPKINLY. - Administer premedication [If Grade 2 or 3 CRS occurs with the second full dose (48 mg) or beyond, administer CRS pre- and post-administration medications with each subsequent dose until a EPKINLY dose is given without subsequent CRS of Grade 2 or higher. Refer to Table 6 for additional information on pre- and post-administration medications.] prior to next dose of EPKINLY. - For the next dose of EPKINLY, monitor more frequently and consider hospitalization.
Grade 3 | Temperature ≥ 100.4°F (38°C) with: Hypotension requiring a vasopressor (with or without vasopressin) and/or Hypoxia requiring high-flow oxygen by nasal cannula, face mask, non-rebreather mask, or Venturi mask. | - Withhold EPKINLY and manage per current practice guidelines, which may include intensive care. - Ensure CRS symptoms are resolved prior to the next dose of EPKINLY. - Administer premedication prior to next dose of EPKINLY. - Hospitalize for the next dose of EPKINLY.
Grade 3 |  | Recurrent Grade 3 CRS; - Permanently discontinue EPKINLY. - Manage CRS per current practice guidelines and provide supportive therapy, which may include intensive care.
Grade 4 | Temperature ≥ 100.4°F (38°C) with: Hypotension requiring multiple vasopressors (excluding vasopressin) and/or Hypoxia requiring oxygen by positive pressure (e.g., CPAP, BiPAP, intubation and mechanical ventilation). | - Permanently discontinue EPKINLY. - Manage CRS per current practice guidelines and provide supportive therapy, which may include intensive care.

Immune Effector Cell-Associated Neurological Toxicity Syndrome (ICANS)

Monitor patients for signs and symptoms of ICANS [see Warnings and Precautions (5.2)]. At the first sign of ICANS, withhold EPKINLY and consider neurology evaluation. Rule out other causes of neurologic symptoms. Provide supportive therapy, which may include intensive care, for ICANS [see Warnings and Precautions (5.2)]. Manage ICANS according to the recommendations in Table 8 and consider further management per current practice guidelines.

Table 8: Recommendations for Management of Immune Effector Cell-Associated Neurotoxicity Syndrome
Grade [Based on American Society for Transplantation and Cellular Therapy (ASTCT) 2019 grading for ICANS.] | Presenting Symptoms [Management is determined by the most severe event, not attributable to any other cause.] | Actions
Grade 1 | ICE score 7-9 [If patient is arousable and able to perform Immune Effector Cell-Associated Encephalopathy (ICE) Assessment, assess: Orientation (oriented to year, month, city, hospital = 4 points); Naming (names 3 objects, e.g., point to clock, pen, button = 3 points); Following Commands (e.g., "show me 2 fingers" or "close your eyes and stick out your tongue" = 1 point); Writing (ability to write a standard sentence = 1 point); and Attention (count backwards from 100 by ten = 1 point). If patient is unarousable and unable to perform ICE Assessment (Grade 4 ICANS) = 0 points.] , Or depressed level of consciousness [Not attributable to any other cause.] : awakens spontaneously. | - Withhold EPKINLY until ICANS resolves. [See Table 4 or Table 5 for recommendations on restarting EPKINLY after dosage delays [see Dosage and Administration (2.3)].] - Monitor neurologic symptoms and consider consultation with neurologist and other specialists for further evaluation and management, including consideration for starting non-sedating, anti-seizure medicines for seizure prophylaxis.
Grade 2 | ICE score 3-6, Or depressed level of consciousness: awakens to voice. | - Withhold EPKINLY until ICANS resolves. - Administer dexamethasone [All references to dexamethasone administration are dexamethasone or equivalent.] 10 mg intravenously every 6 hours. Continue dexamethasone use until resolution to Grade 1 or less, then taper. - Monitor neurologic symptoms and consider consultation with neurologist and other specialists for further evaluation and management, including consideration for starting non-sedating, anti-seizure medicines for seizure prophylaxis.
Grade 3 | ICE score 0-2, Or depressed level of consciousness: awakens only to tactile stimulus, Or seizures, either:; - Any clinical seizure, focal or generalized, that resolves rapidly, or - Non-convulsive seizures on electroencephalogram (EEG) that resolve with intervention,; Or raised intracranial pressure: focal/local edema on neuroimaging. | First Occurrence of Grade 3 ICANS; - Withhold EPKINLY until ICANS resolves. - Administer dexamethasone 10 mg intravenously every 6 hours. Continue dexamethasone use until resolution to Grade 1 or less, then taper. - Monitor neurologic symptoms and consider consultation with neurologist and other specialists for further evaluation and management, including consideration for starting non-sedating, anti-seizure medicines for seizure prophylaxis. - Provide supportive therapy, which may include intensive care.
Grade 3 |  | Recurrent Grade 3 ICANS; - Permanently discontinue EPKINLY - Administer dexamethasone 10 mg intravenously every 6 hours. Continue dexamethasone use until resolution to Grade 1 or less, then taper. - Monitor neurologic symptoms and consider consultation with neurologist and other specialists for further evaluation and management, including consideration for starting non-sedating, anti-seizure medicines for seizure prophylaxis. - Provide supportive therapy, which may include intensive care.
Grade 4 | ICE score 0, Or depressed level of consciousness: either:; - Patient is unarousable or requires vigorous or repetitive tactile stimuli to arouse, or - Stupor or coma; Or seizures, either:; - Life-threatening prolonged seizure (> 5 minutes), or - Repetitive clinical or electrical seizures without return to baseline in between,; Or motor findings:; - Deep focal motor weakness, such as hemiparesis or paraparesis,; or raised intracranial pressure/cerebral edema, with signs/symptoms such as:; - Diffuse cerebral edema on neuroimaging, or - Decerebrate or decorticate posturing, or - Cranial nerve VI palsy, or - Papilledema, or - Cushing's triad. | - Permanently discontinue EPKINLY. - Administer dexamethasone 10 mg intravenously every 6 hours. Continue dexamethasone use until resolution to Grade 1 or less, then taper. - Alternatively, consider administration of methylprednisolone 1,000 mg per day intravenously and continue methylprednisolone 1,000 mg per day intravenously for 2 or more days. - Monitor neurologic symptoms and consider consultation with neurologist and other specialists for further evaluation and management, including consideration for starting non-sedating, anti-seizure medicines for seizure prophylaxis. - Provide supportive therapy, which may include intensive care.

Table 9: Recommended Dosage Modifications for Other Adverse Reactions when EPKINLY is Given as Monotherapy
Adverse Reaction [Based on National Cancer Institute Common Terminology Criteria for Adverse Events (NCI CTCAE), Version 5.0.] | Severity | Action
Infections [see Warnings and Precautions (5.3)] | Grades 1-4 | - Withhold EPKINLY in patients with active infection, until the infection resolves. [See Table 4 or Table 5 for recommendations on restarting EPKINLY after dosage delays [see Dosage and Administration (2.3)].] - For Grade 4, consider permanent discontinuation of EPKINLY.
Neutropenia [see Warnings and Precautions (5.4)] | Absolute neutrophil count less than 0.5 × 10^9/L | - Withhold EPKINLY until absolute neutrophil count is 0.5 × 10^9/L or higher.
Thrombocytopenia [see Warnings and Precautions (5.4)] | Platelet count less than 50 × 10^9/L | - Withhold EPKINLY until platelet count is 50 × 10^9/L or higher.
Other Adverse Reactions [see Adverse Reactions (6.1)] | Grade 3 or higher | - Withhold EPKINLY until the toxicity resolves to Grade 1 or baseline.

Table 10: Recommended Dosage Modifications for Other Adverse Reactions when EPKINLY is Given in Combination with Lenalidomide and Rituximab
Adverse Reaction | Severity [Based on National Cancer Institute Common Terminology Criteria for Adverse Events (NCI CTCAE), Version 5.0.] | Action [Refer to lenalidomide prescribing information for additional toxicity guidelines.]
Neutropenia [see Warnings and Precautions (5.4)] | Absolute neutrophil count less than 0.5 × 10^9/L | - Consider G-CSF. - Withhold EPKINLY until absolute neutrophil count is 1 × 10^9/L or higher. [See Table 4 or 5 for recommendations on restarting EPKINLY after dosage delays [see Dosage and Administration (2.3)].] - Withhold lenalidomide for remainder of cycle. On Day 1 of next cycle, the dose of lenalidomide may be maintained if neutropenia was the only toxicity limiting lenalidomide dosing.
Febrile Neutropenia [see Warnings and Precautions (5.4)] | Grade 3 or higher | - Consider G-CSF. - Withhold EPKINLY until fever resolves and absolute neutrophil count is 1 × 10^9/L or higher. - Withhold lenalidomide for remainder of cycle. On Day 1 of next cycle, dose of lenalidomide may be maintained if febrile neutropenia was the only toxicity limiting lenalidomide dosing.
Thrombocytopenia [see Warnings and Precautions (5.4)] | Platelet count less than 50 × 10^9/L | - Withhold EPKINLY until platelet count is 50 × 10^9/L or higher. - Withhold lenalidomide for remainder of cycle. Decrease lenalidomide dose for next cycle.
Other Adverse Reactions [see Adverse Reactions (6.1)] | Grade 3 | - For first episode, withhold EPKINLY until improvement to Grade 2 or less or resolution to baseline. - For second episode, permanently discontinue EPKINLY if clinically indicated.
Other Adverse Reactions [see Adverse Reactions (6.1)] | Grade 4 | - Permanently discontinue EPKINLY at discretion of healthcare provider.

2.7 Preparation of Diluted EPKINLY using the Vial Method

Read this entire section carefully before preparation of EPKINLY. Certain doses of EPKINLY require dilution prior to administration. Follow the preparation instructions provided below, as improper preparation may lead to improper dose. This section describes preparation of diluted EPKINLY using empty sterile vial method. For preparation using sterile syringe method, see subsection 2.8 [see Dosage and Administration (2.8)].

EPKINLY is prepared and administered by a healthcare provider as a subcutaneous injection. The administration of EPKINLY takes place over the course of 28-day cycles, following the step-up dosage schedule in Section 2.2.

Parenteral drug products should be inspected visually for particulate matter and discoloration prior to administration, whenever solution and container permit.

Use aseptic technique to prepare EPKINLY. Filtration of the diluted solution is not required.

0.16 mg Dose Preparation Instructions (2 dilutions required) – Empty Sterile Vial Method

Use an appropriately sized syringe, vial, and needle for each transfer step.

1. Prepare EPKINLY vial

a. Retrieve one 4 mg/0.8 mL EPKINLY vial from the refrigerator.
b. Allow the vial to come to room temperature for no more than 1 hour.
c. Gently swirl the EPKINLY vial.

DO NOT invert, vortex, or vigorously shake the vial.

2. Perform first dilution

a. Label an appropriately sized empty vial as "Dilution A."
b. Transfer 0.8 mL of EPKINLY into the Dilution A vial.
c. Transfer 4.2 mL of 0.9% Sodium Chloride Injection into the Dilution A vial.
  The initially diluted solution contains 0.8 mg/mL of EPKINLY.
d. Gently swirl the Dilution A vial for 30 to 45 seconds.

3. Perform second dilution

a. Label an appropriately sized empty vial as "Dilution B."
b. Transfer 2 mL of solution from the Dilution A vial into the Dilution B vial. The Dilution A vial is no longer needed.
c. Transfer 8 mL of 0.9% Sodium Chloride Injection into the Dilution B vial to make a final concentration of 0.16 mg/mL.
d. Gently swirl the Dilution B vial for 30 to 45 seconds.

4. Withdraw dose

a. Withdraw 1 mL of the diluted EPKINLY from the Dilution B vial into a syringe.

5. Label syringe

a. Label the syringe with the dose strength (0.16 mg) and the time of day.

Discard the vial containing unused EPKINLY.

0.8 mg Dose Preparation Instructions (1 dilution required) – Empty Sterile Vial Method

Use an appropriately sized syringe, vial, and needle for each transfer step.

1. Prepare EPKINLY vial

a. Retrieve one 4 mg/0.8 mL EPKINLY vial from the refrigerator.
b. Allow the vial to come to room temperature for no more than 1 hour.
c. Gently swirl the EPKINLY vial.

DO NOT invert, vortex, or vigorously shake the vial.

2. Perform dilution

a. Label an appropriately sized empty vial as "Dilution A".
b. Transfer 0.8 mL of EPKINLY into the Dilution A vial.
c. Transfer 4.2 mL of 0.9% Sodium Chloride Injection into the Dilution A vial to make a final concentration of 0.8 mg/mL.
d. Gently swirl the Dilution A vial for 30 to 45 seconds.

3. Withdraw dose

a. Withdraw 1 mL of the diluted EPKINLY from the Dilution A vial into a syringe.

4. Label syringe

a. Label the syringe with the dose strength (0.8 mg) and the time of day.

Discard the vial containing unused EPKINLY.

2.8 Preparation of Diluted EPKINLY using the Syringe Method

Read this entire section carefully before preparation of EPKINLY. Certain doses of EPKINLY require dilution prior to administration. Follow the preparation instructions provided below, as improper preparation may lead to improper dose.

EPKINLY is prepared and administered by a healthcare provider as a subcutaneous injection. The administration of EPKINLY takes place over the course of 28-day cycles, following the step-up dosage schedule in Section 2.2.

Parenteral drug products should be inspected visually for particulate matter and discoloration prior to administration, whenever solution and container permit.

Use aseptic technique to prepare EPKINLY. Filtration of the diluted solution is not required.

0.16 mg Dose Preparation Instructions (2 dilutions required) – Sterile Syringe Method

Use an appropriately sized syringe and needle for each transfer step.

1. Prepare EPKINLY vial

a. Retrieve one 4 mg/0.8 mL EPKINLY vial from the refrigerator.
b. Allow the vial to come to room temperature for no more than 1 hour.
c. Gently swirl the EPKINLY vial.

DO NOT invert, vortex, or vigorously shake the vial.

2. Perform first dilution

a. Label an appropriately sized syringe as "Dilution A."
b. Withdraw 4.2 mL of 0.9% Sodium Chloride Injection into the Dilution A syringe. Include approximately 0.2 mL air in the syringe.
c. In a new syringe labeled as "Syringe 1", withdraw 0.8 mL of EPKINLY.
d. Connect the two syringes and push the 0.8 mL of EPKINLY into the Dilution A syringe. The initially diluted solution contains 0.8 mg/mL of EPKINLY
e. Gently mix by inverting the connected syringes 180 degrees 5 times.
f. Disconnect the syringes and discard Syringe 1.

3. Perform second dilution

a. Label an appropriately sized syringe as "Dilution B."
b. Withdraw 8 mL of 0.9% Sodium Chloride Injection into the Dilution B syringe. Include approximately 0.2 mL air in the syringe.
c. Label another appropriately sized syringe as "Syringe 2."
d. Connect Syringe 2 to the Dilution A syringe and transfer 2 mL of solution into Syringe 2. The Dilution A syringe is no longer needed.
e. Connect Syringe 2 to the Dilution B syringe and push the 2 mL of solution into the Dilution B syringe to make a final concentration of 0.16 mg/mL.
f. Gently mix by inverting the connected syringes 180 degrees 5 times.
g. Disconnect the syringes and discard Syringe 2.

4. Withdraw dose

a. Connect and transfer 1 mL of the diluted EPKINLY from the Dilution B syringe into a new syringe. The Dilution B syringe is no longer needed

5. Label syringe

a. Label the syringe with the dose strength (0.16 mg) and the time of day.

Discard the vial containing unused EPKINLY.

0.8 mg Dose Preparation Instructions (1 dilution required) – Sterile Syringe Method

Use an appropriately sized syringe and needle for each transfer step.

1. Prepare EPKINLY vial

a. Retrieve one 4 mg/0.8 mL EPKINLY vial from the refrigerator.
b. Allow the vial to come to room temperature for no more than 1 hour.
c. Gently swirl the EPKINLY vial.

DO NOT invert, vortex, or vigorously shake the vial.

2. Perform dilution

a. Label an appropriately sized syringe as "Dilution A."
b. Withdraw 4.2 mL of 0.9% Sodium Chloride Injection into the Dilution A syringe. Include approximately 0.2 mL air in the syringe.
c. In a new syringe labeled as "Syringe 1", withdraw 0.8 mL of EPKINLY.
d. Connect the two syringes and push the 0.8 mL of EPKINLY into the Dilution A syringe to make a final concentration of 0.8 mg/mL.
e. Gently mix by inverting the connected syringes 180 degrees 5 times.
f. Disconnect the syringes and discard Syringe 1.

3. Withdraw dose

a. Connect a new syringe to the Dilution A syringe and transfer 1 mL of the diluted EPKINLY into the new syringe. The Dilution A syringe is no longer needed.

4. Label syringe

a. Label the syringe with the dose strength (0.8 mg) and the time of day.

Discard the vial containing unused EPKINLY.

2.9 Preparation of 3 mg and 48 mg EPKINLY Doses

Parenteral drug products should be inspected visually for particulate matter and discoloration prior to administration, whenever solution and container permit.

Use aseptic technique to prepare EPKINLY.

3 mg Dose Preparation Instructions (No dilution required)

EPKINLY 3 mg dose is required for patients with FL only [see Dosage and Administration (2.2)].

1. Prepare EPKINLY vial

a. Retrieve one 4 mg/0.8 mL EPKINLY vial from the refrigerator.
b. Allow the vial to come to room temperature for no more than 1 hour.
c. Gently swirl the EPKINLY vial.

DO NOT invert, vortex, or vigorously shake the vial.

2. Withdraw dose

a. Withdraw 0.6 mL of EPKINLY into a syringe.

3. Label syringe

a. Label the syringe with the dose strength (3 mg) and the time of day.

Discard the vial containing unused EPKINLY.

48 mg Dose Preparation Instructions (No dilution required)

EPKINLY 48 mg/0.8 mL vial is supplied as ready-to-use solution that does not need dilution prior to administration.

1. Prepare EPKINLY vial

a. Retrieve one 48 mg/0.8 mL EPKINLY vial from the refrigerator.
b. Allow the vial to come to room temperature for no more than 1 hour.
c. Gently swirl the EPKINLY vial.

DO NOT invert, vortex, or vigorously shake the vial.

2. Withdraw dose

a. Withdraw 0.8 mL of EPKINLY into a syringe.

3. Label syringe

a. Label the syringe with the dose strength (48 mg) and the time of day.

Discard the vial containing unused EPKINLY.

2.10 Storage and Administration

Storage of EPKINLY Solution in the Syringe

Use EPKINLY solution in the syringe immediately. If not used immediately, store the solution refrigerated at 2°C to 8°C (36°F to 46°F) for up to 24 hours or at room temperature at 20°C to 25°C (68°F to 77°F) for up to 12 hours. The total storage time from the start of dose preparation to administration should not exceed 24 hours. Protect from direct sunlight. Discard unused EPKINLY solution beyond the allowable storage time.

Administration of EPKINLY

To minimize injection pain, allow EPKINLY solution to equilibrate to room temperature for no more than 1 hour before administration. Inject the required volume of EPKINLY into the subcutaneous tissue of the lower part of the abdomen (preferred injection site) or the thigh.

Change of injection site from the left or right side or vice versa is recommended, especially during the weekly administrations (Cycles 1 to 3). Do not inject into tattoos or scars or areas where the skin is red, bruised, tender, hard, or not intact.

3 DOSAGE FORMS AND STRENGTHS

EPKINLY is a clear to slightly opalescent, colorless to slightly yellow solution for subcutaneous injection:

- Injection: 4 mg/0.8 mL in a single-dose vial
- Injection: 48 mg/0.8 mL in a single-dose vial

4 CONTRAINDICATIONS

None.

5 WARNINGS AND PRECAUTIONS

5.1 Cytokine Release Syndrome

EPKINLY can cause CRS, including serious or fatal reactions [see Adverse Reactions (6.1)].

Relapsed or Refractory Large B-cell Lymphoma

CRS occurred in 51% (80/157) of patients with LBCL receiving EPKINLY at the recommended dosage schedule in EPCORE NHL-1, with Grade 1 CRS occurring in 37%, Grade 2 in 17%, and Grade 3 in 2.5% of patients. Recurrent CRS occurred in 31% of these patients. Most CRS events (92%) occurred during Cycle 1. In Cycle 1, CRS events occurred in 6% of patients after the 0.16 mg dose, 12% after the 0.8 mg dose, 43% after the first 48 mg dose, and 5% after the next 48 mg dose. The median time to onset of CRS from the most recent EPKINLY dose was 24 hours (range: 0 to 10 days). The median time to onset after the first 48 mg dose was 21 hours (range: 0 to 7 days).

Patients with DLBCL or high-grade B-cell lymphoma should be hospitalized for 24 hours following administration of the first full 48 mg dose [see Dosage and Administration (2.1, 2.2)].

Relapsed or Refractory Follicular Lymphoma

CRS occurred in 49% (42/86) of patients with FL receiving EPKINLY monotherapy at the recommended dosage schedule in EPCORE NHL-1, with Grade 1 CRS occurring in 45% and Grade 2 in 9% of patients. Recurrent CRS occurred in 48% of patients. Most CRS events (88%) occurred during Cycle 1. In Cycle 1, CRS events occurred in 12% of patients after the 0.16 mg dose, 6% after the 0.8 mg dose, 15% after the 3 mg dose, and 37% after the first 48 mg dose. The median time to onset of CRS from the most recent EPKINLY dose was 59 hours (range: 0.1 to 7 days). The median time to onset after the first 48 mg dose was 61 hours (range: 0.1 to 7 days).

CRS occurred in 24% (32/131) of patients with FL receiving EPKINLY at the recommended dosage schedule in combination with lenalidomide and rituximab in EPCORE FL-1, with Grade 1 CRS occurring in 19%, Grade 2 in 5% of patients, and serious adverse reactions due to CRS in 12%. Recurrent CRS occurred in 41% of patients. Most CRS events (88%) occurred during Cycle 1. In Cycle 1, CRS occurred in 5% of patients after the 0.16 mg dose, 3.8% after the 0.8 mg dose, 2.3% after the 3 mg dose, and 18% after the first 48 mg dose. The median time to onset of CRS from the most recent EPKINLY dose was 78 hours (range: 0.2 to 12 days). The median time to onset after the first 48 mg dose was 41 hours (range: 0.3 to 12 days).

For patients with FL, assess whether hospitalization or outpatient monitoring for the first 48 mg dose is appropriate based on comorbidities or other situational factors [see Dosage and Administration (2.1)]. During outpatient monitoring after the first 48 mg dose, patients should remain in proximity to a healthcare facility that can assess and manage CRS.

Among patients with LBCL or FL who experienced CRS, signs and symptoms included pyrexia, hypotension, hypoxia, dyspnea, chills, and tachycardia. CRS resolved in 98% of patients, after a median duration of 2 days (range: < 1 to 27 days). Concurrent neurological adverse reactions associated with CRS occurred in 2.5% of patients with LBCL, 4.7% of patients with FL receiving EPKINLY monotherapy, and 1.5% of patients receiving EPKINLY in combination with lenalidomide and rituximab. Concurrent neurological adverse reactions included headache, confusional state, tremors, dizziness, and ataxia.

Initiate EPKINLY according to the recommended step-up dosage schedule. Administer pretreatment medications to reduce the risk of CRS and monitor patients for potential CRS accordingly [see Dosage and Administration (2.2, 2.3, 2.4)]. At the first signs or symptoms of CRS, immediately evaluate patients for hospitalization, manage per current practice guidelines, and administer supportive care as appropriate. Withhold or discontinue EPKINLY based on the severity of CRS [see Dosage and Administration (2.6)].

Patients who experience CRS (or other adverse reactions that impair consciousness) should be evaluated and advised not to drive and to refrain from operating heavy or potentially dangerous machinery until resolution.

5.2 Immune Effector Cell-Associated Neurotoxicity Syndrome

EPKINLY can cause life-threatening and fatal immune effector cell-associated neurotoxicity syndrome (ICANS) [see Adverse Reactions (6.1)].

Relapsed or Refractory Large B-cell Lymphoma

ICANS occurred in 6% (10/157) of patients with LBCL receiving EPKINLY at the recommended dosage schedule in EPCORE NHL-1, with Grade 1 ICANS in 4.5% and Grade 2 ICANS in 1.3% of patients. There was one (0.6%) fatal ICANS occurrence. Of the 10 ICANS events, 9 occurred within Cycle 1 of EPKINLY treatment, with a median time to onset of ICANS of 16.5 days (range: 8 to 141 days) from the start of treatment. Relative to the most recent administration of EPKINLY, the median time to onset of ICANS was 3 days (range: 1 to 13 days). The median duration of ICANS was 4 days (range: 0 to 8 days) with ICANS resolving in 90% of patients with supportive care.

Relapsed or Refractory Follicular Lymphoma

ICANS occurred in 6% (8/127) of patients with FL receiving EPKINLY monotherapy following the 2-step up dosage schedule in EPCORE NHL-1, with Grade 1 ICANS in 3.9% and Grade 2 ICANS in 2.4% of patients. The median time to onset of ICANS was 22 days (range: 14 to 66 days) from the start of treatment. Relative to the most recent administration of EPKINLY, the median time to onset of ICANS was 3 days (range: 0.4 to 7 days). The median duration of ICANS was 2 days (range: 1 to 7 days) with ICANS resolving in 100% of patients.

Among patients with FL who received EPINKLY at the recommended dosage schedule in combination with lenalidomide and rituximab in EPCORE FL-1, ICANS occurred in 0.8% (1/131, Grade 1).

For patients with LBCL or FL, clinical manifestations of ICANS included, but were not limited to confusional state, lethargy, tremor, dysgraphia, aphasia, and non-convulsive status epilepticus. The onset of ICANS can be concurrent with CRS, following resolution of CRS, or in the absence of CRS. Monitor patients for potential ICANS following EPKINLY. At the first signs or symptoms of ICANS, immediately evaluate patient and provide supportive therapy based on severity. Withhold or discontinue EPKINLY per recommendations and consider further management per current practice guidelines [see Dosage and Administration (2.6)].

Patients who experience signs or symptoms of ICANS or any other adverse reactions that impair cognition or consciousness should be evaluated, including potential neurology evaluation, and patients at increased risk should be advised not to drive and to refrain from operating heavy or potentially dangerous machinery until resolution.

5.3 Infections

EPKINLY can cause fatal and serious infections [see Adverse Reactions (6.1)].

Serious infections, including opportunistic infections, were reported in 15% of patients with LBCL receiving EPKINLY at the recommended dosage schedule in EPCORE NHL-1 and were most commonly due to sepsis (4.5%) and pneumonia (3.2%). Fatal infections occurred in 1.3% of patients and were due to COVID-19.

Serious infections, including opportunistic infections, were reported in 40% of patients with FL receiving EPKINLY monotherapy following the 2-step up dosage schedule in EPCORE NHL-1 and were most commonly due to COVID-19 (20%), pneumonia (13%), and urinary tract infections (3%). Fatal infections occurred in 6% of patients and included COVID-19 (5%), pneumonia (0.8%), and sepsis (0.8%).

Among 243 patients with FL who received EPKINLY in combination with lenalidomide and rituximab in EPCORE FL-1, serious infections occurred in 28% of patients. The most common serious infections were pneumonia (15%), COVID-19 (7%), opportunistic infections (5%) and upper respiratory infections (3.3%). The most common opportunistic infections of any grade were CMV infection (7%) and herpesvirus infection (7%).

Progressive multifocal leukoencephalopathy (PML), including fatal cases, has occurred in patients treated with EPKINLY. Across a broader clinical trial population, PML was reported in 0.4% (11/3072) of patients, including in the first-line treatment setting. Of the 11 cases of PML, six resulted in fatal outcomes and one was unresolved at the time of death.

Monitor patients for signs and symptoms of infection and treat appropriately. Avoid administration of EPKINLY in patients with active infections. Provide PJP prophylaxis during treatment with EPKINLY, and consider initiating prophylaxis against herpesvirus [see Dosage and Administration (2.5)].

Withhold or consider permanent discontinuation of EPKINLY based on severity [see Dosage and Administration (2.6)].

5.4 Cytopenias

EPKINLY can cause serious or severe cytopenias, including neutropenia, lymphopenia, anemia, and thrombocytopenia [see Adverse Reactions (6.1)].

In patients with LBCL who received EPKINLY at the recommended dosage schedule, Grade 3 or 4 decreased neutrophils occurred in 32% (Grade 4, 14%), decreased hemoglobin in 12% (Grade 4, 0%), and decreased platelets in 12% (Grade 4, 7%) of patients. Febrile neutropenia occurred in 2.5% (Grade 4, 0.6%).

In patients with FL who received EPKINLY monotherapy following the 2-step up dosage schedule, Grade 3 or 4 decreased neutrophils occurred in 30% (Grade 4, 17%), decreased hemoglobin in 10% (Grade 4, 0%), and decreased platelets in 8% of patients (Grade 4, 4%). Febrile neutropenia occurred in 3.1% (Grade 4, 0%).

In patients with FL who received EPKINLY in combination with lenalidomide and rituximab, Grade 3 or 4 decreased neutrophils occurred in 67% (Grade 4, 41%), decreased lymphocytes in 62% (Grade 4, 13%), decreased hemoglobin in 7%, and decreased platelets in 10% (Grade 4, 4.1%) of patients. Febrile neutropenia occurred in 6% (Grade 4, 2.1%).

Monitor complete blood counts throughout treatment. Based on the severity of cytopenias, temporarily withhold or permanently discontinue EPKINLY [see Dosage and Administration (2.6)]. Consider prophylactic granulocyte colony-stimulating factor administration as applicable.

5.5 Embryo-Fetal Toxicity

Based on its mechanism of action, EPKINLY may cause fetal harm when administered to a pregnant woman. Advise pregnant women of the potential risk to the fetus. Advise females of reproductive potential to use effective contraception during treatment with EPKINLY and for 4 months after the last dose [see Use in Specific Populations (8.1, 8.3)].

6 ADVERSE REACTIONS

The following clinically significant adverse reactions are described elsewhere in the labeling:

- Cytokine Release Syndrome [see Warnings and Precautions (5.1)].
- Immune Effector Cell-Associated Neurotoxicity Syndrome [see Warnings and Precautions (5.2)].
- Infections [see Warnings and Precautions (5.3)].
- Cytopenias [see Warnings and Precautions (5.4)].

6.1 Clinical Trials Experience

Because clinical trials are conducted under widely varying conditions, adverse reaction rates observed in the clinical trials of a drug cannot be directly compared to rates in the clinical trials of another drug and may not reflect the rates observed in practice.

Relapsed or Refractory Large B-cell Lymphoma (LBCL)

EPCORE NHL-1

The safety of EPKINLY was evaluated in EPCORE NHL-1, a single-arm study of patients with relapsed or refractory LBCL after two or more lines of systemic therapy, including DLBCL not otherwise specified, DLBCL arising from indolent lymphoma, high grade B-cell lymphoma, and other B-cell lymphomas [see Clinical Studies (14.1)]. A total of 157 patients with LBCL received EPKINLY via subcutaneous injection until disease progression or unacceptable toxicities according to the following 28-day cycle schedule:

- Cycle 1: EPKINLY 0.16 mg on Day 1, 0.8 mg on Day 8, 48 mg on Days 15 and 22
- Cycles 2-3: EPKINLY 48 mg on Days 1, 8, 15, and 22
- Cycles 4-9: EPKINLY 48 mg on Days 1 and 15
- Cycles 10 and beyond: EPKINLY 48 mg on Day 1

Of the 157 patients treated, the median age was 64 years (range: 20 to 83), 60% were male, and 97% had an ECOG performance status of 0 or 1. Race was reported in 133 (85%) patients; of these patients, 61% were White, 19% were Asian, and 0.6% were Native Hawaiian or Other Pacific Islander. There were no Black or African American or Hispanic or Latino patients treated in the clinical trial as reported. The median number of prior therapies was 3 (range: 2 to 11). The study excluded patients with CNS involvement of lymphoma, allogeneic HSCT or solid organ transplant, an ongoing active infection, and any patients with known impaired T-cell immunity.

The median duration of exposure for patients receiving EPKINLY was 5 cycles (range: 1 to 20 cycles).

Serious adverse reactions occurred in 54% of patients who received EPKINLY. Serious adverse reactions in ≥ 2% of patients included CRS, infections (including sepsis, COVID-19, pneumonia, and upper respiratory tract infections), pleural effusion, febrile neutropenia, fever, and ICANS. Fatal adverse reactions occurred in 3.8% of patients who received EPKINLY, including COVID-19 (1.3%), hepatotoxicity (0.6%), ICANS (0.6%), myocardial infarction (0.6%), and pulmonary embolism (0.6%).

Permanent discontinuation of EPKINLY due to an adverse reaction occurred in 3.8% of patients. Adverse reactions which resulted in permanent discontinuation of EPKINLY included COVID-19, CRS, ICANS, pleural effusion, and fatigue.

Dosage interruptions of EPKINLY due to an adverse reaction occurred in 34% of patients who received EPKINLY. Adverse reactions which required dosage interruption in ≥ 3% of patients included CRS, neutropenia, sepsis, and thrombocytopenia.

The most common (≥ 20%) adverse reactions were CRS, fatigue, musculoskeletal pain, injection site reactions, pyrexia, abdominal pain, nausea, and diarrhea. The most common Grade 3 to 4 laboratory abnormalities (≥ 10%) were decreased lymphocyte count, decreased neutrophil count, decreased white blood cell count, decreased hemoglobin, and decreased platelets.

Table 11 summarizes the adverse reactions in EPCORE NHL-1.

Table 11: Adverse Reactions (≥ 10%) in Patients with Relapsed or Refractory LBCL Who Received EPKINLY in EPCORE NHL-1
 | EPKINLY (N=157)
Adverse Reaction [Adverse reactions were graded based on CTCAE Version 5.0] | All Grades (%) | Grade 3 or 4 (%)
Immune system disorders
Cytokine release syndrome [CRS was graded using ASTCT consensus criteria (Lee et al., 2019).] | 51 | 2.5 [Only grade 3 adverse reactions occurred.]
General disorders and administration site conditions
Fatigue [Fatigue includes asthenia, fatigue, lethargy.] | 29 | 2.5
Injection site reactions [Injection site reaction includes injection site erythema, injection site hypertrophy, injection site inflammation, injection site mass, injection site pain, injection site pruritus, injection site rash, injection site reaction, injection site swelling, injection site urticaria.] | 27 | 0
Pyrexia | 24 | 0
Edema [Edema includes edema, edema peripheral, face edema, generalized edema, peripheral swelling.] | 14 | 1.9
Musculoskeletal and connective tissue disorders
Musculoskeletal pain [Musculoskeletal pain includes back pain, bone pain, flank pain, musculoskeletal chest pain, musculoskeletal pain, myalgia, neck pain, non-cardiac chest pain, pain, pain in extremity, spinal pain.] | 28 | 1.3
Gastrointestinal disorders
Abdominal pain [Abdominal pain includes abdominal discomfort, abdominal pain, abdominal pain lower, abdominal pain upper, abdominal tenderness.] | 23 | 1.9
Diarrhea | 20 | 0
Nausea | 20 | 1.3
Vomiting | 12 | 0.6
Skin and subcutaneous disorders
Rash [Rash includes dermatitis bullous, erythema, palmar erythema, penile erythema, rash, rash erythematous, rash maculo-papular, rash pustular, recall phenomenon, seborrheic dermatitis, skin exfoliation.] | 15 | 0.6
Nervous system disorder
Headache | 13 | 0.6
Metabolism and nutrition disorders
Decreased appetite | 12 | 0.6
Cardiac disorders
Cardiac arrhythmias [Cardiac arrhythmias includes bradycardia, sinus bradycardia, sinus tachycardia, supraventricular extrasystoles, supraventricular tachycardia, tachycardia.] | 10 | 0.6

Clinically relevant adverse reactions in < 10% of patients who received EPKINLY included ICANS, sepsis, pleural effusion, COVID-19, pneumonia (including pneumonia and COVID-19 pneumonia), tumor flare, febrile neutropenia, upper respiratory tract infections, and tumor lysis syndrome.

Table 12 summarizes laboratory abnormalities in EPCORE NHL-1.

Table 12: Select Laboratory Abnormalities (≥ 20%) That Worsened from Baseline in Patients with Relapsed or Refractory LBCL Who Received EPKINLY in EPCORE NHL-1
Laboratory Abnormality [Laboratory abnormalities were graded based on CTCAE Version 5.0] | EPKINLY [The denominator used to calculate the rate varied from 146 to 153 based on the number of patients with a baseline value and at least one post-treatment value.]
Laboratory Abnormality [Laboratory abnormalities were graded based on CTCAE Version 5.0] | All Grades (%) | Grade 3 or 4 (%)
Hematology
Lymphocyte count decreased | 87 | 77
Hemoglobin decreased | 62 | 12
White blood cells decreased | 53 | 22
Neutrophils decreased | 50 | 32
Platelets decreased | 48 | 12
Chemistry
Sodium decreased | 56 | 2.6
Phosphate decreased [CTCAE Version 5.0 does not include numeric thresholds for grading of hypophosphatemia; all grades represent patients with lab value < Lower Limit of Normal (LLN).] | 56 | N/A
Aspartate aminotransferase increased | 48 | 4.6
Alanine aminotransferase increased | 45 | 5.3
Potassium decreased | 34 | 5.3
Magnesium decreased | 31 | 0
Creatinine increased | 24 | 3.3
Potassium increased | 21 | 1.3

Relapsed or Refractory Follicular Lymphoma (FL)

EPCORE FL-1

The safety of EPKINLY in combination with lenalidomide and rituximab was evaluated in EPCORE FL-1, an open-label, randomized, multicenter trial that included patients with relapsed or refractory FL after at least one line of systemic therapy [see Clinical Studies (14.2)]. The study excluded patients with transformed lymphoma, absolute neutrophil count < 1.0 × 10^9/L, platelet count < 70 × 10^9/L (or < 50 × 10^9/L if bone marrow infiltration by lymphoma or splenomegaly), known active infection, creatinine clearance < 50 mL/min, alanine or aspartate transaminase > 3 times the upper limit of normal, and clinically significant cardiovascular disease. Patients were randomized to receive EPKINLY in combination with lenalidomide and rituximab (N=243) or lenalidomide and rituximab alone (N=238). Patients received EPKINLY via subcutaneous injection in 28-day cycles for a total of 12 cycles or until disease progression or unacceptable toxicity, whichever occurred first. Of the 243 patients who received EPKINLY, 131 received the recommended 3 step-up dosage schedule.

The recommended EPKINLY dosage schedule was:

- Cycle 1: EPKINLY 0.16 mg on Day 1, 0.8 mg on Day 8, 3 mg on Day 15, and 48 mg on Day 22
- Cycles 2-3: EPKINLY 48 mg on Days 1, 8, 15, and 22
- Cycles 4-12: EPKINLY 48 mg on Day 1

In both treatment arms, lenalidomide was given orally at a dose of 20 mg once daily from Days 1 to 21 for 12 cycles. Rituximab was administered intravenously at a dose of 375 mg/m^2 on Days 1, 8, 15, and 22 of Cycle 1, followed by administration on Day 1 of Cycles 2 to 5.

Safety results are based on all 243 patients who received EPKINLY, with the exception of data for CRS and ICANS which are based on patients who received EPKINLY at the recommended dosage schedule. The median duration of exposure in this arm was 10 cycles for EPKINLY and 9 cycles for lenalidomide.

Serious adverse reactions occurred in 51% of these patients, including serious infections in 28% of patients and serious CRS in 12% of patients. Fatal adverse reactions within 60 days of last treatment occurred in 0.8% of patients.

Adverse reactions led to permanent discontinuation of EPKINLY in 6% of patients and dose interruption in 75% of patients, with infection as a leading cause. Adverse reactions leading to interruption of EPKINLY in ≥ 5% of patients included respiratory tract infections, CRS, and rash.

In the EPKINLY arm, adverse reactions led to lenalidomide dose interruption in 72%, dose reduction in 22%, and permanent discontinuation in 15%.

The most common (≥ 20%) adverse reactions in the EPKINLY arm were rash, upper respiratory tract infections, fatigue, injection site reactions, constipation, diarrhea, CRS, pneumonia, COVID-19, and fever. The most common Grade 3 to 4 laboratory abnormalities (≥ 10%) were decreases in neutrophil count, lymphocyte count, and platelets.

Table 13 summarizes select adverse reactions in EPCORE FL-1.

Table 13: Adverse Reactions (≥ 10% All Grade and ≥ 5% Higher) in Patients with Relapsed or Refractory FL Who Received EPKINLY in Combination with Lenalidomide and Rituximab in EPCORE FL-1
Adverse Reaction [Adverse reactions were graded using CTCAE Version 5.0. CRS was graded using ASTCT consensus criteria (Lee et al., 2019).] | EPKINLY + Lenalidomide and Rituximab |  | Lenalidomide and Rituximab
Adverse Reaction [Adverse reactions were graded using CTCAE Version 5.0. CRS was graded using ASTCT consensus criteria (Lee et al., 2019).] | All Grades (%) | Grade 3 or 4 (%) | All Grades (%) | Grade 3 or 4 (%)
 | (N=131) |  | (N=238)
Immune system disorders
Cytokine release syndrome | 24 [The frequency of CRS is based on 131 patients who received EPKINLY at the recommended dosage schedule [see Dosage and Administration (2.2)]. Grade 1 CRS: 19%; Grade 2 CRS: 5%.] [The frequency of CRS among the 243 patients who received either the 2-step up or 3-step up dosage schedule was the following: Any grade CRS 35%; Grade 1 CRS: 28%; Grade 2 CRS: 7%.] | 0 | 0.8 | 0
 | (N=243) |  | (N=238)
Skin and subcutaneous tissue disorders
Rash [Rash includes blister, dermatitis, erythema, rash, skin exfoliation, skin reaction, toxic skin eruption, urticaria and related terms.] | 46 | 11 [Only Grade 3 adverse reactions occurred.] | 34 | 6
Infections and infestations
Upper respiratory tract infections [Upper respiratory tract infections include sinusitis, laryngitis, nasopharyngitis, pharyngitis, rhinitis, rhinovirus infection, upper respiratory tract infection, and related terms.] | 33 | 3.3 | 18 | 0.4
Pneumonia [Pneumonia includes pneumonia, COVID-19 pneumonia, pneumonia fungal, Pneumocystis jirovecii pneumonia, pneumonia cytomegaloviral, and related terms.] | 24 | 16 | 8 [Includes one case with a fatal outcome.] | 4.6
COVID-19 [COVID-19 includes COVID-19, COVID-19 pneumonia, coronavirus infection, coronavirus pneumonia.] | 23 | 5 | 13 | 1.3
General disorders and administration site conditions
Fatigue [Fatigue includes asthenia, fatigue, lethargy, malaise.] | 31 | 4.9 | 24 | 2.1
Injection site reactions | 27 | 0 | 0.4 | 0
Fever | 23 | 0.4 | 11 | 1.3
Gastrointestinal disorders
Constipation | 26 | 0.8 | 21 | 0
Mucositis [Mucositis includes gingival pain, glossitis, mouth ulceration, mucosal infection, mucosal inflammation, oral discomfort, oral mucosal exfoliation, oropharyngeal pain, stomatitis.] | 12 | 0 | 3.4 | 0
Nervous system disorders
Neurological changes [Neurological changes include brain fog, cognitive disorder, confusional state, disturbance in attention, dysphonia, epilepsy, essential tremor, gait disturbance, hypoacusis, lethargy, loss of consciousness, memory impairment, somnolence, syncope, tremor, vertigo, and ICANS.] | 15 | 1.2 | 8 | 1.3
Headache | 11 | 0 | 3.8 | 0
Psychiatric disorders
Insomnia | 14 | 0 | 2.9 | 0
This table includes a combination of grouped and ungrouped terms.

Other clinically relevant adverse reactions include:

Gastrointestinal disorders: diarrhea (26%), nausea (16%), abdominal pain (11%), vomiting (4.1%)

Musculoskeletal and connective tissue disorders: musculoskeletal pain (14%), arthralgia (8%)

Nervous system disorders: peripheral neuropathy (12%), dizziness (7%), ICANS (0.8%)

General disorders: edema (12%)

Infections: cytomegalovirus infection (7%), herpesvirus infection (7%), sepsis (2.9%)

Blood and lymphatic system disorders: febrile neutropenia (6%)

Neoplasms: tumor flare (1.2%)

Table 14 summarizes laboratory abnormalities in EPCORE FL-1. Grade 4 laboratory abnormalities in ≥ 2% of the EPKINLY arm included decreases in neutrophils (41%), lymphocytes (13%), and platelets decreased (4.1%).

Table 14: Select Laboratory Abnormalities (≥ 30% All Grade and ≥ 10% Higher) That Worsened from Baseline in Patients with Relapsed or Refractory FL Who Received EPKINLY in Combination with Lenalidomide and Rituximab in EPCORE FL-1
Laboratory Abnormality | EPKINLY + Lenalidomide and Rituximab [The denominator used to calculate the rate varied from 240 to 242 in the EPKINLY arm, and 225 to 236 in the comparator arm, based on the number of patients with a baseline value and at least one post-treatment value.] |  | Lenalidomide and Rituximab
Laboratory Abnormality | All Grades (%) | Grade 3 or 4 (%) | All Grades (%) | Grade 3 or 4 (%)
Hematology
Neutrophils decreased | 86 | 67 | 75 | 41
Lymphocytes decreased | 86 | 62 | 56 | 15
Hemoglobin decreased | 66 | 7 | 52 | 4.7
Platelets decreased | 50 | 10 | 37 | 7
Chemistry
Alanine aminotransferase increased | 58 | 7 | 36 | 0.9
Phosphate decreased [CTCAE Version 5.0 does not include numeric thresholds for grading of hypophosphatemia; all grades represent patients with lab value < Lower Limit of Normal (LLN).] | 49 | N/A | 28 | N/A
Sodium decreased | 43 | 4.1 | 23 | 2.6
Potassium decreased | 41 | 9 | 20 | 4.7
Aspartate aminotransferase increased | 40 | 2.9 | 29 | 0.9
Laboratory abnormalities were graded based on CTCAE Version 5.0

EPCORE NHL-1

The safety of EPKINLY as monotherapy was evaluated in EPCORE NHL-1, a single-arm study of patients with relapsed or refractory FL after two or more lines of systemic therapy who received EPKINLY following a 2-step up dosage schedule (N=127) [see Clinical Studies (14.2)]. A separate dose optimization cohort evaluated the recommended 3-step up dosage schedule for CRS mitigation (N=86), where EPKINLY was administered via subcutaneous injection until disease progression or unacceptable toxicities according to the following 28-day cycle schedule:

- Cycle 1: EPKINLY 0.16 mg on Day 1, 0.8 mg on Day 8, 3 mg on Day 15, and 48 mg on Day 22
- Cycle 2-3: EPKINLY 48 mg on Days 1, 8, 15, and 22
- Cycles 4-9: EPKINLY 48 mg on Days 1 and 15
- Cycles 10 and beyond: EPKINLY 48 mg on Day 1

With the exception of CRS, the safety results presented below and in Tables 15 and 16 represent data from patients who received the 2-step up dosage schedule. The data presented for CRS reflects the 86 patients who received the recommended 3-step up dosage schedule. The study excluded patients with CNS involvement of lymphoma, allogeneic HSCT or solid organ transplant, ongoing active infection, any patients with known impaired T-cell immunity, creatinine clearance < 45 ml/min, alanine aminotransferase > 3 times the upper limit of normal, and a cardiac ejection fraction < 45%.

Recommended 3-step up Dosage Schedule

Of the 86 patients with relapsed or refractory FL who received EPKINLY following the recommended 3-step up dosage schedule, the median age was 63 years (range: 33 to 90), 57% were male, and 100% had an ECOG performance status of 0 or 1.

The median duration of exposure was 5 cycles (range: 1 to 12 cycles). CRS occurred in 49% of patients, with Grade 1 CRS occurring in 45% and Grade 2 in 9% of patients. Serious adverse reactions due to CRS occurred in 28% of patients who received EPKINLY. Dose interruptions due to CRS occurred in 19% of patients who received EPKINLY.

2-step up Dosage Schedule

Of the 127 patients with relapsed or refractory FL who received EPKINLY following a 2-step up dosage schedule, the median age was 65 years (range: 39 to 84), 62% were male, and 95% had an ECOG performance status of 0 or 1 [see Clinical Studies (14.2)]. The median duration of exposure for patients receiving EPKINLY was 8 cycles (range: 1 to 33 cycles).

Serious adverse reactions occurred in 66% of patients who received EPKINLY. Serious adverse reactions in ≥ 5% of patients included CRS, COVID-19, pneumonia, and second primary malignancies.

Fatal adverse reactions occurred in 9% of patients who received EPKINLY, including COVID-19 (5%), pneumonitis (1.6%), cardiac failure (0.8%), pneumonia (0.8%), and sepsis (0.8%).

Permanent discontinuation of EPKINLY due to an adverse reaction occurred in 19% of patients who received EPKINLY. Adverse reactions which resulted in permanent discontinuation of EPKINLY in ≥ 2% of patients included COVID-19, Hepatitis E, pneumonitis, and second primary malignancy.

Dosage interruptions of EPKINLY due to an adverse reaction occurred in 59% of patients who received EPKINLY. Adverse reactions which required dosage interruption in ≥ 5% of patients included COVID-19, CRS, pneumonia, upper respiratory tract infection, and fatigue.

The most common (≥ 20%) adverse reactions were injection site reactions, CRS, COVID-19, fatigue, upper respiratory tract infection, musculoskeletal pain, rash, diarrhea, pyrexia, cough, and headache. The most common Grade 3 to 4 laboratory abnormalities (≥ 10%) were decreased lymphocyte count, decreased neutrophil count, decreased white blood cell count, and decreased hemoglobin.

Table 15 summarizes the adverse reactions in EPCORE NHL-1.

Table 15: Adverse Reactions (≥ 10%) in Patients with Relapsed or Refractory FL Who Received EPKINLY as Monotherapy in EPCORE NHL-1
Adverse Reaction [Adverse reactions were graded based on CTCAE Version 5.0.] | EPKINLY
Adverse Reaction [Adverse reactions were graded based on CTCAE Version 5.0.] | All Grades (%) | Grade 3 or 4 (%)
(N=86) [The frequency of CRS is based on 86 patients with FL who received the recommended 3-step up dosage schedule in EPCORE NHL-1 [see Dosage and Administration (2.2)].]
Immune system disorders
Cytokine release syndrome [CRS was graded using ASTCT consensus criteria (Lee et al., 2019).] [The frequency of CRS based on the 127 patients with FL who received the 2-step up dosage schedule in EPCORE NHL-1 was the following: Any grade CRS 66%; Grade 1 CRS: 50%; Grade 2 CRS: 26%; Grade 3 CRS: 1.6%.] | 49 | 0
(N=127)
General disorders and administration site conditions
Injection site reactions [Includes related grouped terms.] | 58 | 0
Fatigue | 37 | 5 [Only Grade 3 adverse reactions occurred.]
Pyrexia | 26 | 2
Edema | 17 | 0
Infections and Infestations
COVID-19 [COVID-19 includes COVID-19, COVID-19 pneumonia, SARS-CoV-2 test positive.] | 40 | 19
Upper respiratory tract infection [Upper respiratory tract infection includes preferred terms with upper respiratory infection and sinusitis, laryngitis viral, nasopharyngitis, oropharyngitis fungal, pharyngitis, rhinitis, rhinovirus infection, tonsillitis.] | 29 | 2
Pneumonia [Pneumonia includes preferred terms with pneumonia, bronchopulmonary aspergillosis, infectious pleural effusion, infective exacerbation of bronchiectasis, Pneumocystis jirovecii pneumonia, pneumonia respiratory syncytial viral.] | 17 | 13
Urinary tract infection | 13 | 5
Herpesvirus infection [Herpesvirus infection includes herpes simplex, herpes simplex reactivation, herpes virus infection, herpes zoster, oral herpes, varicella zoster virus infection.] | 12 | 1.6
Musculoskeletal and connective tissue disorders
Musculoskeletal pain | 28 | 0.8
Arthralgia | 14 | 0.8
Skin and subcutaneous disorders
Rash | 28 | 0
Gastrointestinal disorders
Diarrhea | 26 | 1.6
Nausea | 17 | 0
Abdominal pain | 17 | 0.8
Constipation | 16 | 0
Mucositis [Mucositis includes aphthous ulcer, mouth ulceration, mucosal inflammation, oral pain, oropharyngeal pain, stomatitis, tongue ulceration.] | 12 | 0
Respiratory disorders
Cough | 20 | 0
Dyspnea | 17 | 0
Nervous system disorders
Headache | 20 | 0
Neurological changes [Neurological changes includes amnesia, aphasia, balance disorder, brain fog, confusional state, dysphonia, encephalopathy, extrapyramidal disorder, hallucination, hypoacusis, memory impairment, mental status changes, tremor, vertigo.] | 13 | 0
Peripheral neuropathy and paresthesia [Peripheral neuropathy and paresthesia includes bell's palsy, hypoesthesia, neuralgia, neuropathy peripheral, paresthesia, peripheral sensory neuropathy, polyneuropathy.] | 13 | 1.6
Dizziness | 11 | 0
Psychiatric disorders
Insomnia | 13 | 0
Renal and urinary disorders
Renal insufficiency [Renal insufficiency includes acute kidney injury, blood creatinine increased, renal impairment.] | 10 | 1.6

Clinically relevant adverse reactions in < 10% of patients (N=127) who received EPKINLY included vomiting, pruritus, hepatotoxicity, ICANS, lower respiratory tract infections, cardiac arrhythmias, respiratory tract infections, pneumonitis, second primary malignancy, vision changes, cellulitis, febrile neutropenia, cardiac failure, cytomegalovirus infection and sepsis.

Table 16 summarizes laboratory abnormalities in EPCORE NHL-1.

Table 16: Select Laboratory Abnormalities (≥ 20%) That Worsened from Baseline in Patients with Relapsed or Refractory FL Who Received EPKINLY in EPCORE NHL-1
Laboratory Abnormality [Laboratory abnormalities were graded based on CTCAE Version 5.0] | EPKINLY [The denominator used to calculate the rate varied from 123 to 127 based on the number of patients with a baseline value and at least one post-treatment value.] (N=127)
Laboratory Abnormality [Laboratory abnormalities were graded based on CTCAE Version 5.0] | All Grades | Grade 3 or 4 (%)
Hematology
Lymphocytes decreased | 94 | 82
Hemoglobin decreased | 59 | 10
White blood cells decreased | 58 | 19
Neutrophils decreased | 55 | 30
Platelets decreased | 49 | 8
Chemistry
Sodium decreased | 51 | 1.6
ALT increased | 47 | 8
AST increased | 44 | 6
Creatinine increased | 36 | 0.8
Alkaline phosphatase increased | 29 | 0
Bilirubin increased | 28 | 1.6
Potassium decreased | 20 | 3.1
Magnesium decreased | 20 | 0.8

6.2 Postmarketing Experience

The following adverse reaction has been identified during post-approval use of EPKINLY. Because these reactions are reported voluntarily from a population of uncertain size, it is not always possible to reliably estimate their frequency or establish a causal relationship to drug exposure.

- Immune system disorders: Hemophagocytic Lymphohistiocytosis (HLH)

7 DRUG INTERACTIONS

For certain CYP substrates, minimal changes in the concentration may lead to serious adverse reactions. Monitor for toxicity or drug concentrations of such CYP substrates when co-administered with EPKINLY.

Epcoritamab-bysp causes release of cytokines [see Clinical Pharmacology (12.2)] that may suppress activity of CYP enzymes, resulting in increased exposure of CYP substrates. Increased exposure of CYP substrates is more likely to occur after the first dose of EPKINLY and up to 14 days after the first 48 mg dose, and during and after CRS [see Warnings and Precautions (5.1)].

8 USE IN SPECIFIC POPULATIONS

8.1 Pregnancy

Risk Summary

Based on the mechanism of action, EPKINLY may cause fetal harm when administered to a pregnant woman [see Clinical Pharmacology (12.1)]. There are no available data on the use of EPKINLY in pregnant women to evaluate for a drug-associated risk. No animal reproductive or developmental toxicity studies have been conducted with epcoritamab-bysp.

Epcoritamab-bysp causes T-cell activation and cytokine release; immune activation may compromise pregnancy maintenance. In addition, based on expression of CD20 on B-cells and the finding of B-cell depletion in non-pregnant animals, epcoritamab-bysp can cause B-cell lymphocytopenia in infants exposed to epcoritamab-bysp in-utero. Human immunoglobulin G (IgG) is known to cross the placenta; therefore, EPKINLY has the potential to be transmitted from the mother to the developing fetus. Advise women of the potential risk to the fetus.

In the U.S. general population, the estimated background risk of major birth defects and miscarriage in clinically recognized pregnancies is 2% to 4% and 15% to 20%, respectively.

8.2 Lactation

Risk Summary

There is no information regarding the presence of epcoritamab-bysp in human milk, the effect on the breastfed child, or milk production. Because maternal IgG is present in human milk, and there is potential for epcoritamab-bysp absorption leading to serious adverse reactions in a breastfed child, advise women not to breastfeed during treatment with EPKINLY and for 4 months after the last dose.

8.3 Females and Males of Reproductive Potential

EPKINLY may cause fetal harm when administered to a pregnant woman [see Use in Specific Populations (8.1)].

Pregnancy Testing

Verify pregnancy status in females of reproductive potential prior to initiating EPKINLY.

Contraception

Females

Advise females of reproductive potential to use effective contraception during treatment with EPKINLY and for 4 months after the last dose.

8.4 Pediatric Use

The safety and efficacy of EPKINLY in pediatric patients have not been established.

8.5 Geriatric Use

LBCL

In patients with relapsed or refractory LBCL who received EPKINLY in EPCORE NHL-1, 77 (49%) were 65 years of age and older, and 29 (19%) were 75 years of age or older. No clinically meaningful differences in safety or efficacy were observed between patients with relapsed or refractory LBCL who were 65 years of age and older compared with younger adult patients.

FL

In patients with relapsed or refractory FL who received EPKINLY in combination with lenalidomide and rituximab in EPCORE FL-1, 88 (36%) were 65 years of age or older and 20 (8%) were 75 years of age or older. No clinically meaningful differences in safety or efficacy were observed between patients who were 65 years of age and older compared with younger patients.

In patients with relapsed or refractory FL who received EPKINLY in EPCORE NHL-1, 66 (52%) were 65 years of age or older, and 16 (13%) were 75 years of age and older.

In patients with relapsed or refractory FL, there was a higher rate of fatal adverse reactions, primarily infections, including COVID-19, in patients older than 65 years of age compared to younger adult patients. No overall difference in efficacy was observed in patients with relapsed or refractory FL who were 65 years of age and older compared with younger patients.

11 DESCRIPTION

Epcoritamab-bysp is a bispecific CD20-directed CD3 T-cell engager; it is a humanized bispecific IgG1 antibody. Epcoritamab-bysp is manufactured in Chinese hamster ovary (CHO) cells using recombinant DNA technology and has an approximate molecular weight of 149 kDa.

EPKINLY (epcoritamab-bysp) injection for subcutaneous use is a sterile, preservative-free, clear to slightly opalescent, colorless to slightly yellow solution, free of visible particles.

Each single-dose 4 mg/0.8 mL vial contains epcoritamab-bysp (4 mg), acetic acid (0.19 mg), polysorbate 80 (0.32 mg), sodium acetate (1.7 mg), sorbitol (21.9 mg) and Water for Injection, USP. The pH is 5.5.

Each single-dose 48 mg/0.8 mL vial contains epcoritamab-bysp (48 mg), acetic acid (0.19 mg), polysorbate 80 (0.32 mg), sodium acetate (1.7 mg), sorbitol (21.9 mg) and Water for Injection, USP. The pH is 5.5.

12 CLINICAL PHARMACOLOGY

12.1 Mechanism of Action

Epcoritamab-bysp is a T-cell engaging bispecific antibody that binds to the CD3 receptor expressed on the surface of T-cells and CD20 expressed on the surface of lymphoma cells and healthy B-lineage cells.

In vitro, epcoritamab-bysp activated T-cells, caused the release of proinflammatory cytokines, and induced lysis of B-cells.

In nonclinical studies, the combination of epcoritamab-bysp and rituximab resulted in both T-cell mediated cytotoxicity and natural killer (NK) cell mediated antibody-dependent cellular cytotoxicity (ADCC).

12.2 Pharmacodynamics

Circulating B-Cell Count

Circulating B-cells decreased to undetectable levels (< 10 cells/microliter) after administration of the approved recommended dosage of EPKINLY in patients who had detectable B-cells at treatment initiation by Cycle 1 Day 15 and the depletion was sustained while patients remained on treatment.

Cytokine Concentrations

Plasma concentrations of cytokines (IL-2, IL-6, IL-10, TNF-α, and IFN-γ) were measured. Transient elevation of circulating cytokines was observed at dose levels of 0.04 mg and above.

After administration of the approved recommended dosages of EPKINLY, cytokine levels increased within 24 hours after the first dose on Cycle 1 Day 1, generally reached maximum levels after the first 48 mg dose, and returned to baseline prior to the second 48 mg full dose.

12.3 Pharmacokinetics

Pharmacokinetic (PK) parameters were evaluated at the approved recommended dosage (48 mg) and are presented as geometric mean (CV%) unless otherwise specified.

Epcoritamab-bysp area under the concentration-time curve (AUC) increased more than proportionally over a full dosage range from 1.5 to 60 mg (0.03125 to 1.25 times the approved recommended dosage).

Epcoritamab-bysp maximum concentration (10.2 mcg/mL [43.2%]) is achieved after the first dose of the Q2W regimen (i.e., the first dose of Cycle 4). No clinically significant differences in pharmacokinetic parameters were observed between patients with relapsed or refractory LBCL and patients with relapsed or refractory FL. PK exposures are summarized for the recommended dosage of EPKINLY in Table 17.

Table 17: Exposure Parameters of Epcoritamab-bysp in Subjects with Relapsed or Refractory LBCL or FL Following Recommended Dosage
 | Cavg (mcg/mL) [Values are geometric mean with geometric CV%.] | Cmax (mcg/mL) | Ctrough (mcg/mL)
First full 48 mg dose [First full 48 mg dose is on the first day of Week 3 in subjects with relapsed or refractory LBCL and on the first day of Week 4 in subjects with relapsed or refractory FL.] | 1.3 (113.3%) | 1.7 (106.7%) | 1.4 (100.9%)
End of weekly dosing (end of Cycle 3) | 9.1 (45.9%) | 9.9 (43.4%) | 7.8 (52.4%)
End of every 2-week dosing (end of Cycle 9) | 5.3 (57%) | 6.7 (49.4%) | 3.6 (81.5%)
Steady state [Steady state values are approximated at Cycle 15 (Week 60).] with every 4-week dosing | 2.4 (73.3%) | 4.2 (59.8%) | 1.1 (134.1%)

Absorption

The median (range) Tmax of epcoritamab-bysp after the first full dose and end of the weekly dosing regimen (end of Cycle 3) treatment doses were 4 (0.3 to 7) days and 2.3 (0.3 to 3.2) days, respectively.

Distribution

The apparent total volume of distribution is 25.6 L (82%).

Elimination

The half-life of full dose epcoritamab-bysp (48 mg) was approximately 22 days (58%) at the end of Cycle 3, with apparent total clearance of approximately 0.53 L/day (40%) after the end of Cycle 3.

Metabolism

Epcoritamab-bysp is expected to be metabolized into small peptides by catabolic pathways.

Specific Populations

No clinically significant differences in the PK of epcoritamab-bysp were observed based on age (20 to 89 years), sex, race (White or Asian), mild to moderate renal impairment (creatinine clearance [CLcr] 30 to < 90 mL/min as estimated by Cockcroft-Gault formula), and mild hepatic impairment (total bilirubin ≤ ULN and AST > ULN, or total bilirubin 1 to 1.5 times ULN and any AST) after accounting for differences in bodyweight.

The effects of severe renal impairment (CLcr 15 to < 30 mL/min), end-stage renal disease (CLcr < 15 mL/min), or moderate to severe hepatic impairment (total bilirubin > 1.5 times ULN and any AST) on the PK of epcoritamab-bysp are unknown.

Body Weight

In patients who received the recommended dosage of EPKINLY, geometric mean average concentration following the first full 48 mg dose was 31% lower in the higher body weight (BW) group (85 to 172 kg) and 13% higher in the lower BW group (39 to 65 kg) compared to patients with BW of 65 to less than 85 kg.

Drug Interaction Studies

No clinical studies evaluating the drug interaction potential of epcoritamab-bysp have been conducted.

12.6 Immunogenicity

The observed incidence of anti-drug antibodies is highly dependent on the sensitivity and specificity of the assay. Differences in assay methods preclude meaningful comparisons of the incidence of anti-drug antibodies (ADA) in the study described below with the incidence of ADA in other studies, including those of epcoritamab-bysp.

Anti-epcoritamab-bysp antibodies developed in 2.6% of patients (4 of 156) with LBCL and 4.2% of patients (8 of 190) with FL treated with EPKINLY in EPCORE NHL-1 (up to 10 cycles) [see Clinical Studies (14.1, 14.2)] using an electrochemiluminescence immunoassay (ECLIA). Anti-epcoritamab-bysp antibodies developed in 2.1% of patients (5 of 236) with FL treated with EPKINLY in combination with lenalidomide and rituximab in EPCORE FL-1 (up to 12 cycles) [see Clinical Studies (14.2)] using an ECLIA. Because of the low occurrence of anti-drug antibodies, the effect of these antibodies on the PK, pharmacodynamics, safety, and effectiveness of epcoritamab-bysp is unknown.

13 NONCLINICAL TOXICOLOGY

13.1 Carcinogenesis, Mutagenesis, Impairment of Fertility

No carcinogenicity or genotoxicity studies have been conducted with epcoritamab-bysp.

No dedicated studies have been conducted to evaluate the effects of epcoritamab-bysp on fertility.

14 CLINICAL STUDIES

14.1 DLBCL and High-grade B-cell Lymphoma

The efficacy of EPKINLY was evaluated in EPCORE NHL-1 (Study GCT3013-01; NCT03625037), an open-label, multi-cohort, multicenter, single-arm trial in 157 patients with relapsed or refractory large B-cell lymphoma (LBCL) after two or more lines of systemic therapy. The study excluded patients with CNS involvement of lymphoma, allogeneic HSCT or solid organ transplant, ongoing active infection, and any patients with known impaired T-cell immunity. Patients received EPKINLY monotherapy at the recommended 2-step up dosage schedule:

- Cycle 1: EPKINLY 0.16 mg on Day 1, 0.8 mg on Day 8, 48 mg on Days 15 and 22
- Cycles 2-3: EPKINLY 48 mg on Days 1, 8, 15, and 22
- Cycles 4-9: EPKINLY 48 mg on Days 1 and 15
- Cycles 10 and beyond: EPKINLY 48 mg on Day 1

Patients continued to receive EPKINLY until disease progression or unacceptable toxicity. In the setting of a suspected tumor flare reaction, continued treatment was permitted.

The efficacy population includes 148 patients with DLBCL, not otherwise specified (NOS), including DLBCL arising from indolent lymphoma, and high-grade B-cell lymphoma. Of the 148 patients, the median age was 65 years (range: 22 to 83), 62% were male, 97% had an ECOG performance status of 0 or 1, and 3% had an ECOG performance status of 2. Race was reported in 125 (84%) patients; of these patients, 61% were White, 20% were Asian, and 0.7% were Native Hawaiian or Other Pacific Islander. There were no Black or African American or Hispanic or Latino patients treated in the clinical trial as reported. The diagnosis was DLBCL NOS in 86%, including 27% with DLBCL transformed from indolent lymphoma, and high-grade B-cell lymphoma in 14%. The median number of prior therapies was 3 (range: 2 to 11), with 30% receiving 2 prior therapies, 30% receiving 3 prior therapies, and 40% receiving 4 or more prior therapies. Eighteen percent had prior autologous HSCT, and 39% had prior chimeric antigen receptor (CAR) T-cell therapy. Eighty-two percent of patients had disease refractory to last therapy and 29% of patients were refractory to CAR T-cell therapy.

Efficacy was established based on overall response rate (ORR) and duration of response as assessed by an Independent Review Committee (IRC) using Lugano 2014 criteria. The efficacy results are summarized in Table 18.

Table 18: Efficacy Results in EPCORE NHL-1 in Patients with DLBCL and High-grade B-cell Lymphoma
Endpoint [Determined by Lugano criteria (2014) as assessed by independent review committee (IRC).] | EPKINLY (N=148)
ORR [Early response assessments were evaluated in the context of potential flare reactions. Of 90 patients who achieved an objective response, 9 patients had early flare reactions identified with objective response demonstrated on subsequent imaging per Lugano criteria.] , n (%) | 90 (61)
(95% CI) | (52.5, 68.7)
CR, n (%) | 56 (38)
(95% CI) | (30.0, 46.2)
PR, n (%) | 34 (23)
(95% CI) | (16.5, 30.6)
DOR
Median (95% CI), months | 15.6 (9.7, NR)
9-month estimate [Kaplan-Meier estimate.] (95% CI), % | 63 (51.5, 72.4)
ORR = overall response rate; CI = confidence interval; CR = complete response; PR = partial response; DOR = duration of response; NR = not reached.

The median time to response was 1.4 months (range: 1 to 8.4 months). Among responders, the median follow-up for DOR was 9.8 months (range: 0.0 to 17.3 months).

14.2 Follicular Lymphoma

EPKINLY in Combination with Lenalidomide and Rituximab for FL

The efficacy of EPKINLY in combination with lenalidomide and rituximab was evaluated in EPCORE FL-1 (Study M20-638; NCT05409066), an open-label, randomized, multicenter, global trial in patients with relapsed or refractory FL after at least one line of systemic therapy. Patients were randomized to receive EPKINLY in combination with lenalidomide and rituximab, or lenalidomide and rituximab alone. The study excluded patients with known CNS involvement by lymphoma, prior allograft, and known active infection. Patients received EPKINLY via subcutaneous injection in 28-day cycles for a total of 12 cycles or until disease progression or unacceptable toxicity, whichever occurred first.

The recommended EPKINLY dosage schedule was:

- Cycle 1: EPKINLY 0.16 mg on Day 1, 0.8 mg on Day 8, 3 mg on Day 15 and 48 mg on Day 22
- Cycles 2-3: EPKINLY 48 mg on Days 1, 8, 15, and 22
- Cycles 4-12: EPKINLY 48 mg on Day 1

In both treatment arms, lenalidomide was given orally at a dose of 20 mg once daily from Days 1 to 21 for 12 cycles and Rituximab was administered intravenously at a dose of 375 mg/m^2 on Days 1, 8, 15, and 22 of Cycle 1, followed by administration on Day 1 of Cycles 2 to 5.

Of all patients randomized, the median age was 61 years (range: 24 to 89 years), with 40% being age 65 or older; 57% were male; 72% were White, 24% Asian, and 2% were Black; and 98% had an ECOG performance status of 0 or 1. The median number of prior lines of systemic therapy was 1 (range: 1 to 7) with 24% receiving 2 prior lines and 17% receiving 3 or more prior lines of therapy. Forty-one percent had progressive disease within 24 months of first systemic therapy.

Efficacy was established based on progression free survival (PFS) and overall response rate (ORR) as assessed by Independent Review Committee (IRC) using Lugano 2014 criteria.

The efficacy results, based on a prespecified interim analysis, are summarized in Table 19 and the Kaplan-Meier plot of PFS presented in Figure 1. The results are based on a median duration of follow-up of 10.4 months in the intention-to-treat population.

Table 19: Efficacy Results in EPCORE FL-1 in Patients with FL
Outcome per IRC | EPKINLY + Lenalidomide and Rituximab (N=243) | Lenalidomide and Rituximab (N=245)
PFS
Number of events, n (%) | 23 (9) | 75 (31)
Progressive disease | 19 (83) | 63 (84)
Death | 4 (17) | 12 (16)
Median (95% CI), months | NR (21.9, NR) | 11.2 (10.5, NR)
Hazard ratio [Cox proportional hazards hazard ratio stratified by disease history and region.] (95% CI) | 0.21 (0.13, 0.33)
P-value [Log-rank p-value (one sided) stratified by disease history and region.] | < 0.0001
ORR, n (%) | 216 (89) | 181 (74)
(95% CI) | (84, 93) | (68, 79)
P-value [P-value is based on a prespecified analysis of the first 232 patients randomized.] , [P-value (one sided) is from a Cochran-Mantel-Haenszel test stratified by disease history and region.] | < 0.0001
CR, n (%) | 181 (74) | 106 (43)
(95% CI) | (69, 80) | (37, 50)
P-value | < 0.0001
PFS = progression free survival; CI = confidence interval; NR = not reached; ORR = overall response rate; CR = complete response.

Figure 1: Kaplan-Meier Plot of PFS per IRC

After a median duration of follow-up of 14.8 months overall, the median overall survival had not been reached in either arm with a total of 35 deaths: 10 (4%) deaths in the EPKINLY arm and 25 (10%) deaths in the lenalidomide and rituximab arm.

EPKINLY as Monotherapy for FL

The efficacy of EPKINLY as monotherapy was evaluated in EPCORE NHL-1 (Study GCT3013-01; NCT03625037), an open-label, multi-cohort, multicenter, single-arm trial that included patients with relapsed or refractory follicular lymphoma (FL) after at least 2 lines of systemic therapy. The study excluded patients with CNS involvement of lymphoma, allogeneic HSCT or solid organ transplant, ongoing active infection, any patients with known impaired T-cell immunity, creatinine clearance < 45 mL/min, alanine aminotransferase > 3 times the upper limit of normal, and a cardiac ejection fraction < 45%. Patients received EPKINLY monotherapy following a 2-step up dosage schedule:

- Cycle 1: EPKINLY 0.16 mg on Day 1, 0.8 mg on Day 8, 48 mg on Days 15 and 22
- Cycles 2-3: EPKINLY 48 mg on Days 1, 8, 15, and 22
- Cycles 4-9: EPKINLY 48 mg on Days 1 and 15
- Cycles 10 and beyond: EPKINLY 48 mg on Day 1

Patients continued to receive EPKINLY until disease progression or unacceptable toxicity.

Among the 127 patients with FL, the median age was 65 years (range: 39 to 84), 52% were 65 years of age or older, and 62% were male. Race was reported in 85 (67%) patients; of these patients, 89% were White, and 8% were Asian. A total of 85% had stage III-IV disease, 25% had bulky disease, 95% had an ECOG performance status of 0 or 1, and 6% had an ECOG performance status of 2. The median number of prior therapies was 3 (range: 2 to 9), with 36% receiving 2 prior lines of systemic therapy, 32% receiving 3 prior therapies, and 32% receiving 4 or more prior therapies.

Seventy-nine percent of patients were refractory to prior anti-CD20 monoclonal antibody therapy, 70% were refractory to both anti-CD20 monoclonal antibody and alkylator therapy, 21% had prior rituximab plus lenalidomide therapy, 19% received prior autologous HSCT, and 5% received prior chimeric antigen receptor (CAR) T-cell therapy. Fifty-two percent of patients had progression of disease within 24 months of first systemic therapy.

Efficacy was established based on overall response rate (ORR) determined by Lugano 2014 criteria as assessed by Independent Review Committee (IRC) and duration of response. The median follow-up for DOR was 14.8 months. The efficacy results are summarized in Table 20.

Table 20: Efficacy Results in EPCORE NHL-1 in Patients with FL
Endpoint [Determined by Lugano criteria (2014) as assessed by independent review committee (IRC).] | EPKINLY (N=127)
ORR, n (%) | 104 (82)
(95% CI) | (74.1, 88.2)
CR, n (%) | 76 (60)
(95% CI) | (50.8, 68.4)
PR, n (%) | 28 (22)
(95% CI) | (15.2, 30.3)
DOR
Median (95% CI), months | NR (13.7, NR)
12-month estimate [Kaplan-Meier estimate.] % (95% CI) | 68.4 (57.6, 77.0)
ORR = overall response rate; CI = confidence interval; CR = complete response; PR = partial response; DOR = duration of response; NR = not reached.

The median time to first response was 1.4 months (range: 1 to 3 months).

In a separate dose optimization cohort in EPCORE NHL-1, 86 patients received the recommended 3-step up dosage schedule in Cycle 1 [see Adverse Reactions (6.1)]. The efficacy results in this cohort were comparable to the primary efficacy population.

16 HOW SUPPLIED/STORAGE AND HANDLING

How Supplied

EPKINLY (epcoritamab-bysp) injection is a sterile, preservative-free, clear to slightly opalescent, colorless to slightly yellow solution, free of visible particles, supplied in glass vials as follows:

Carton contents | NDC number
One 4 mg/0.8 mL single-dose vial | NDC 82705-002-01
One 48 mg/0.8 mL single-dose vial | NDC 82705-010-01

The vial stopper is not made with natural rubber latex.

Storage and Handling

Store refrigerated at 2°C to 8°C (36°F to 46°F). Keep in the original carton to protect from light. Do not freeze. Do not shake.

17 PATIENT COUNSELING INFORMATION

Advise the patient to read the FDA-approved patient labeling (Medication Guide).

Cytokine Release Syndrome (CRS)

Inform patients of the risk of CRS, and to immediately contact their healthcare provider should signs and symptoms associated with CRS (e.g., pyrexia, hypotension, hypoxia, chills, tachycardia, headache, and dyspnea) occur at any time. Advise patients with DLBCL or high-grade B-cell lymphoma that they should be hospitalized for 24 hours after administration of the Cycle 1 Day 15 dosage of 48 mg. Advise patients with FL that they may be hospitalized after administration of the Cycle 1 Day 22 dosage of 48 mg. Patients who receive Cycle 1 Day 22 dosage of 48 mg at an outpatient facility should remain in proximity of a healthcare facility that can assess and manage CRS afterwards. Advise all patients who experience symptoms that impair consciousness not to drive and refrain from operating heavy or potentially dangerous machinery until events resolve [see Warnings and Precautions (5.1)].

Immune Effector Cell-Associated Neurotoxicity Syndrome (ICANS)

Advise patients of the risk of ICANS, to immediately contact their healthcare provider for signs and symptoms associated with ICANS, which may manifest, for example, as confusional state, lethargy, tremor, dysgraphia, aphasia, and non-convulsive status epilepticus, and that the onset of events may be delayed. Advise patients who experience symptoms of ICANS that impair consciousness to refrain from driving or operating heavy or potentially dangerous machinery until symptoms of ICANS resolve [see Warnings and Precautions (5.2)].

Infections

Advise patients of the risk of serious infections, and to contact their healthcare professional for signs or symptoms of serious infection [see Warnings and Precautions (5.3)].

Cytopenias

Discuss the signs and symptoms associated with cytopenias, including neutropenia and febrile neutropenia, anemia, and thrombocytopenia [see Warnings and Precautions (5.4)].

Embryo-Fetal Toxicity

Advise pregnant women of the potential risk to a fetus. Advise females of reproductive potential to inform their healthcare provider if they are pregnant or become pregnant [see Use in Specific Populations (8.1)]. Advise females of reproductive potential to use effective contraception during treatment with EPKINLY and for 4 months after the last dose [see Use in Specific Populations (8.3)].

Lactation

Advise women not to breastfeed during treatment with EPKINLY and for 4 months after the last dose [see Use in Specific Populations (8.2)].

Manufactured by:
Genmab US, Inc.
Plainsboro, NJ 08536, USA
1-855-4GENMAB (1-855-443-6622)
U.S. License Number: 2293

Marketed by:
Genmab US, Inc.
Plainsboro, NJ 08536
and
AbbVie Inc.
North Chicago, IL 60064

EPKINLY is a registered trademark owned by Genmab A/S

©2025 Genmab A/S

MEDICATION GUIDE
EPKINLY® (ep-KIN-lee)
(epcoritamab-bysp)
injection, for subcutaneous use

What is the most important information I should know about EPKINLY?
EPKINLY can cause serious side effects, including:

- Cytokine Release Syndrome (CRS). CRS is common during treatment with EPKINLY and can also be serious or lead to death. Tell your healthcare provider or get medical help right away if you develop any signs or symptoms of CRS, including:

- fever of 100.4°F (38°C) or higher
- dizziness or light-headedness
- trouble breathing
- chills
- fast heartbeat
- feeling anxious

- headache
- confusion
- shaking (tremors)
- problems with balance and movement, such as trouble walking

Due to the risk of CRS, you will receive EPKINLY on a "step-up dosing schedule".

- The step-up dosing schedule is when you receive 2 or 3 smaller "step-up" doses of EPKINLY during your first cycle of treatment (Cycle 1).
- You will receive your first full dose of EPKINLY a week after your last step-up dose (this will be Day 15 or Day 22 of Cycle 1).
- If your dose of EPKINLY is delayed for any reason, you may need to repeat the "step-up dosing schedule".
- Before each dose in Cycle 1, you will receive medicines to help reduce your risk of CRS. You will also receive medicine for 3 days after each dose in Cycle 1. Your healthcare provider will decide if you need to receive medicine to help reduce your risk of CRS with future cycles.
- See "How will I receive EPKINLY?" for more information about how you will receive EPKINLY.

- Neurologic problems. EPKINLY can cause serious neurologic problems that can be life-threatening and lead to death. Neurologic problems may happen days or weeks after you receive EPKINLY. Your healthcare provider may refer you to a healthcare provider who specializes in neurologic problems. Tell your healthcare provider right away if you develop any signs or symptoms of neurologic problems, including:

- trouble speaking or writing
- confusion and disorientation
- drowsiness
- tiredness or lack of energy

- muscle weakness
- shaking (tremors)
- seizures
- memory loss

Your healthcare provider will monitor you for signs and symptoms of CRS and neurologic problems during treatment with EPKINLY, as well as other side effects and treat you if needed. Your healthcare provider may temporarily stop or completely stop your treatment with EPKINLY if you develop CRS, neurologic problems, or any other side effects that are severe.
People with diffuse large B-cell lymphoma (DLBCL) or high-grade B-cell lymphoma should be hospitalized for 24 hours after receiving their first full dose of EPKINLY on Day 15 of Cycle 1 due to the risk of CRS and neurologic problems.
People with follicular lymphoma (FL) may need to be hospitalized after receiving their first full dose of EPKINLY on Day 22 of Cycle 1 due to the risk of CRS.
See "What are the possible side effects of EPKINLY?" for more information about side effects.

What is EPKINLY?
EPKINLY is a prescription medicine used to treat adults with:

- certain types of DLBCL or high-grade B-cell lymphoma that has come back (relapsed) or that did not respond (refractory),after 2 or more treatments.
- follicular lymphoma that has come back or that did not respond to previous treatment, together with lenalidomide and rituximab.
- follicular lymphoma that has come back or that did not respond after 2 or more treatments.

It is not known if EPKINLY is safe and effective in children.

Before receiving EPKINLY, tell your healthcare provider about all of your medical conditions, including if you:

- have an infection.
- are pregnant or plan to become pregnant. EPKINLY may harm your unborn baby.
  Females who are able to become pregnant:
  - Your healthcare provider should do a pregnancy test before you start treatment with EPKINLY.
  - You should use effective birth control (contraception) during treatment and for 4 months after your last dose of EPKINLY.
  - Tell your healthcare provider if you become pregnant or think that you may be pregnant during treatment with EPKINLY.
- are breastfeeding or plan to breastfeed. It is not known if EPKINLY passes into your breast milk. Do not breastfeed during treatment and for 4 months after your last dose of EPKINLY.

Tell your healthcare provider about all the medicines you take, including prescription and over-the-counter medicines, vitamins, and herbal supplements.

How will I receive EPKINLY?

- EPKINLY will be given to you by your healthcare provider as an injection under your skin (subcutaneous injection), usually in the lower part of your stomach-area (abdomen) or thigh.
- Your EPKINLY treatment schedule is divided into cycles that are usually 28 days (4 weeks) long.
- Your healthcare provider will decide how many treatment cycles you will receive and how often you will receive EPKINLY in each cycle.
- See "What is the most important information I should know about EPKINLY?" for more information about how you will receive EPKINLY.

What should I avoid while receiving EPKINLY?
Do not drive, operate heavy machinery, or do other dangerous activities if you develop dizziness, confusion, tremors, sleepiness, or any other symptoms that impair consciousness until your signs and symptoms go away. These may be signs and symptoms of CRS or neurologic problems.
See "What is the most important information I should know about EPKINLY?" for more information about signs and symptoms of CRS and neurologic problems.

What are the possible side effects of EPKINLY?
EPKINLY can cause serious side effects, including:

- See "What is the most important information I should know about EPKINLY?"
- Infections. EPKINLY can cause serious infections that may lead to death. Your healthcare provider will check you for signs and symptoms of infection before and during treatment with EPKINLY. Your healthcare provider should prescribe medicines before you start treatment to help prevent infection and treat you as needed if you develop an infection during treatment with EPKINLY. Tell your healthcare provider right away if you develop any signs or symptoms of infection during treatment with EPKINLY, including:

- fever of 100.4°F (38°C) or higher
- cough
- chest pain
- tiredness
- shortness of breath

- painful rash
- sore throat
- pain during urination
- feeling weak or generally unwell
- confusion

- Low blood cell counts. EPKINLY can cause low blood cell counts which can be serious or severe. Your healthcare provider will check your blood cell counts during treatment with EPKINLY. EPKINLY may cause the following low blood cell counts:
  - low white blood cell counts (neutropenia and lymphopenia). Low white blood cells can increase your risk for infection.
  - low red blood cell counts (anemia). Low red blood cells can cause tiredness and shortness of breath.
  - low platelet counts (thrombocytopenia). Low platelet counts can cause bruising or bleeding problems.

Your healthcare provider may temporarily stop or completely stop treatment with EPKINLY if you develop certain side effects.
The most common side effects of EPKINLY when used alone in DLBCL or high-grade B-cell lymphoma or FL include:

- CRS
- injection site reactions
- tiredness

- muscle and bone pain
- fever
- diarrhea

- COVID-19
- rash
- stomach area (abdominal pain)

The most common severe abnormal laboratory test results with EPKINLY when used alone in DLBCL or high-grade B-cell lymphoma or FL include: decreased white blood cells, decreased red blood cells, and decreased platelets.

The most common side effects of EPKINLY when used together with lenalidomide and rituximab in follicular lymphoma include:

- rash
- upper respiratory tract infections
- tiredness
- injection site reactions

- constipation
- diarrhea
- CRS

- pneumonia
- COVID-19
- fever

The most common severe abnormal laboratory test results with EPKINLY when used together with lenalidomide and rituximab in follicular lymphoma include: decreased white blood cells and decreased platelets.
These are not all of the possible side effects of EPKINLY.
Call your doctor for medical advice about side effects. You may report side effects to FDA at 1-800-FDA-1088.

General information about safe and effective use of EPKINLY.
Medicines are sometimes prescribed for purposes other than those listed in a Medication Guide. You can ask your pharmacist or healthcare provider for information about EPKINLY that is written for health professionals.

What are the ingredients in EPKINLY?
Active ingredient: epcoritamab-bysp
Inactive ingredients: acetic acid, polysorbate 80, sodium acetate, sorbitol and Water for Injection.
Manufactured by: Genmab US, Inc., Plainsboro, NJ 08536
U.S. License Number: 2293
Marketed by: Genmab US, Inc., Plainsboro, NJ 08536 and AbbVie Inc., North Chicago, IL 60064
EPKINLY is a registered trademark owned by Genmab A/S
©2025 Genmab A/S
For more information, go to www.EPKINLY.com or call 1-855-4GENMAB (1-855-443-6622)

This Medication Guide has been approved by the U.S. Food and Drug Administration.

Revised: Nov 2025

PRINCIPAL DISPLAY PANEL - 48 mg/0.8 mL Vial Carton

NDC 82705-010-01
Rx only

epkinly®
(epcoritamab-bysp)
Injection

48 mg/0.8 mL

For subcutaneous injection
by a healthcare provider only.

Provide enclosed Medication
Guide to patient.

One single-dose vial.
Discard unused portion.

Genmab
abbvie

PRINCIPAL DISPLAY PANEL - 4 mg/0.8 mL Vial Carton

NDC 82705-002-01
Rx only

epkinly®
(epcoritamab-bysp)
Injection

4 mg/0.8 mL

For subcutaneous injection
by a healthcare provider only.

Provide enclosed Medication
Guide to patient.

One single-dose vial.
Discard unused portion.

Genmab
abbvie